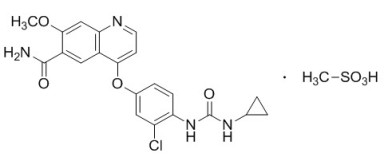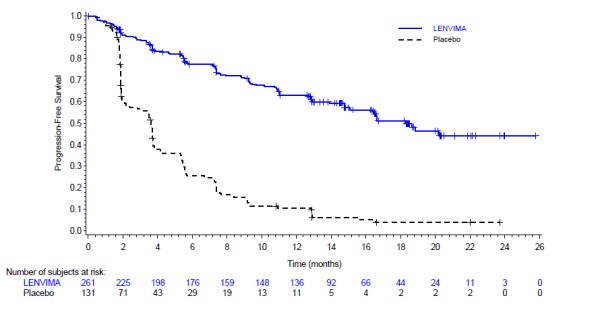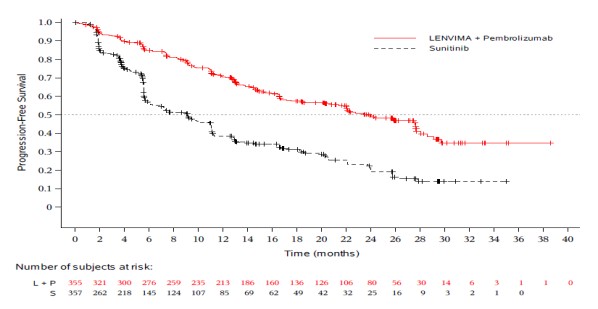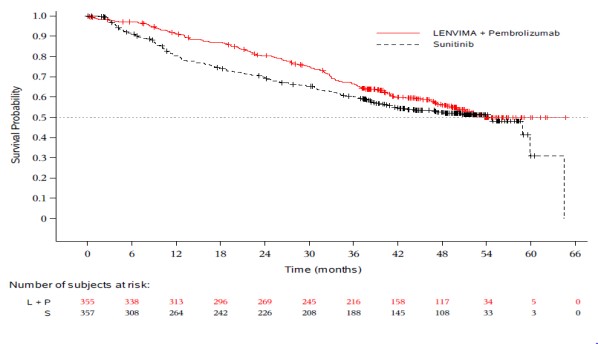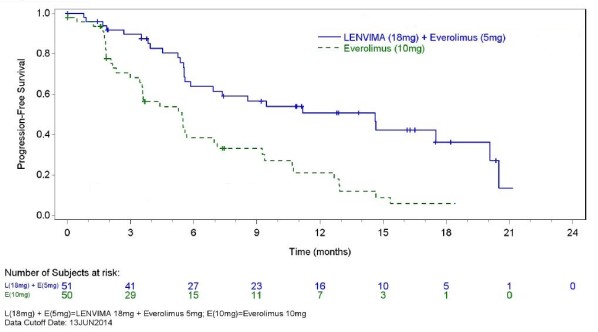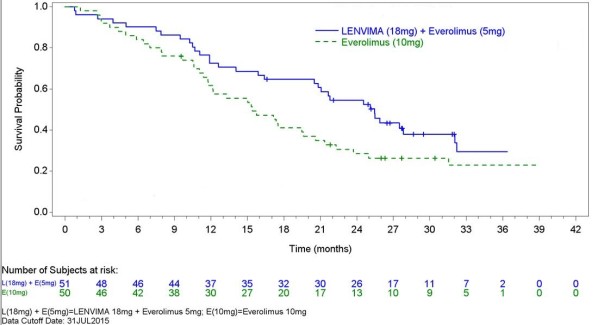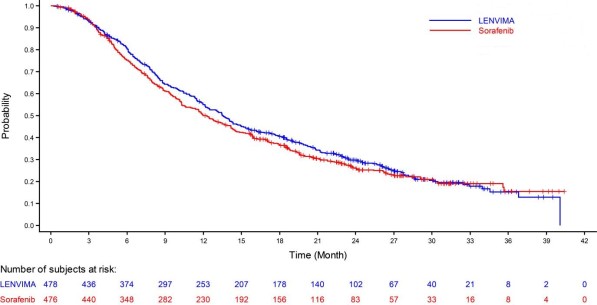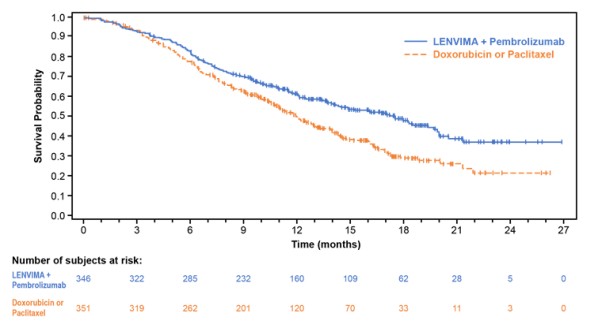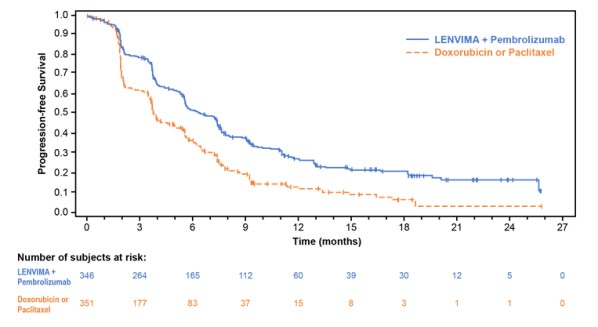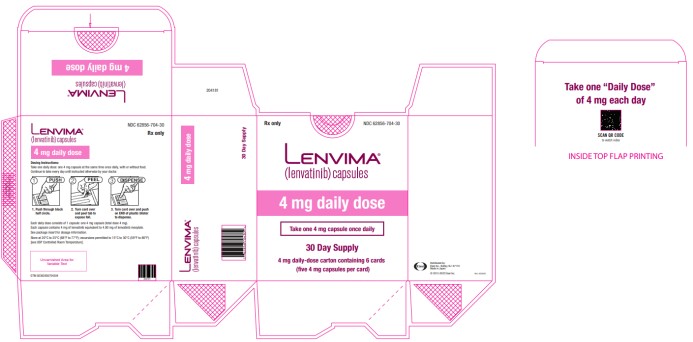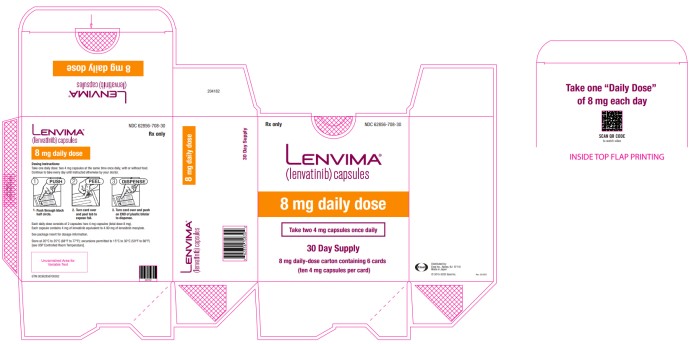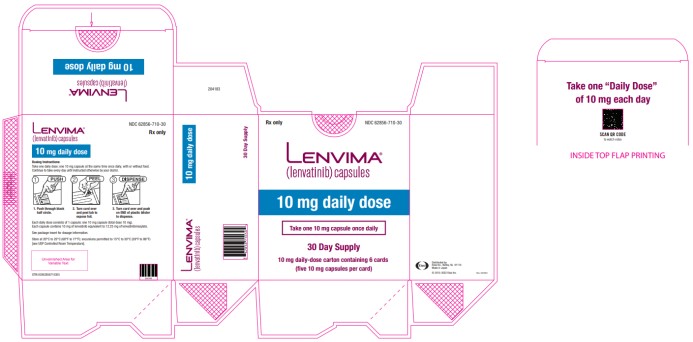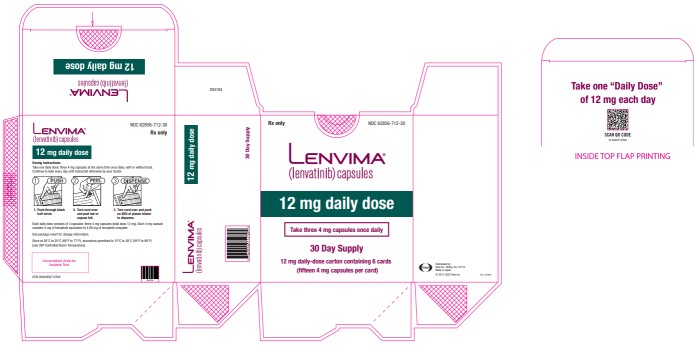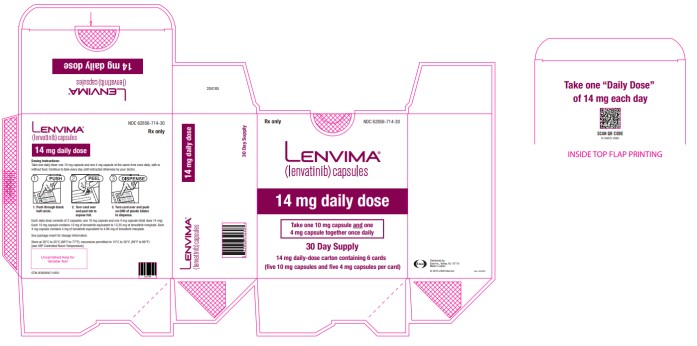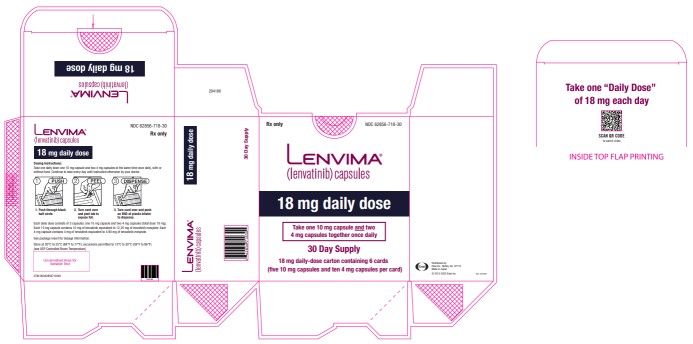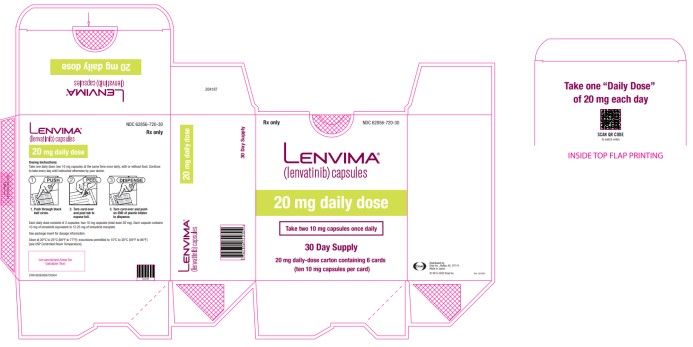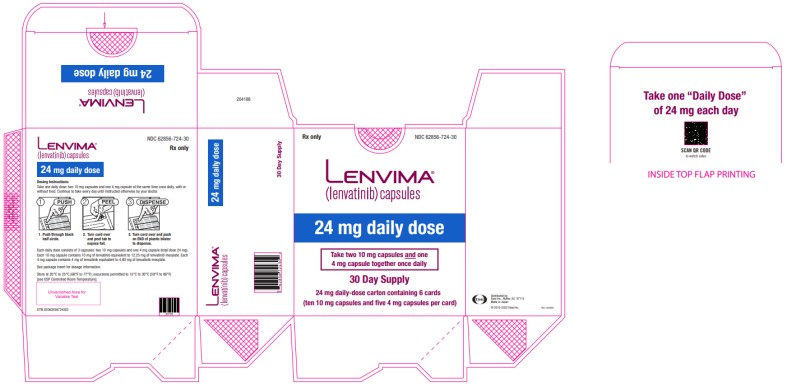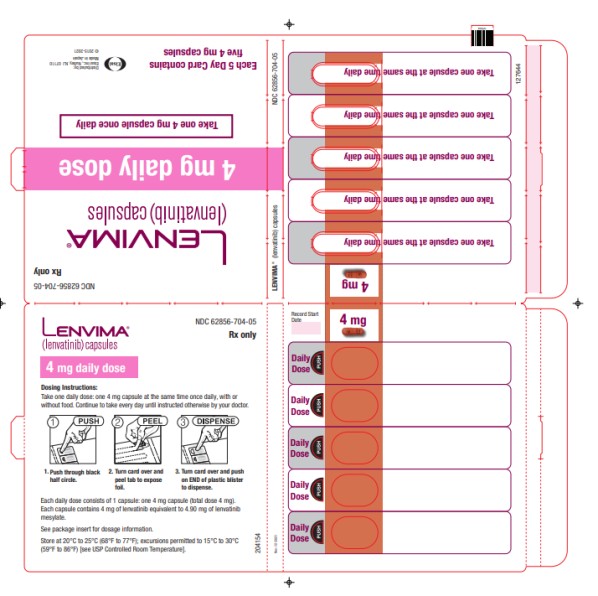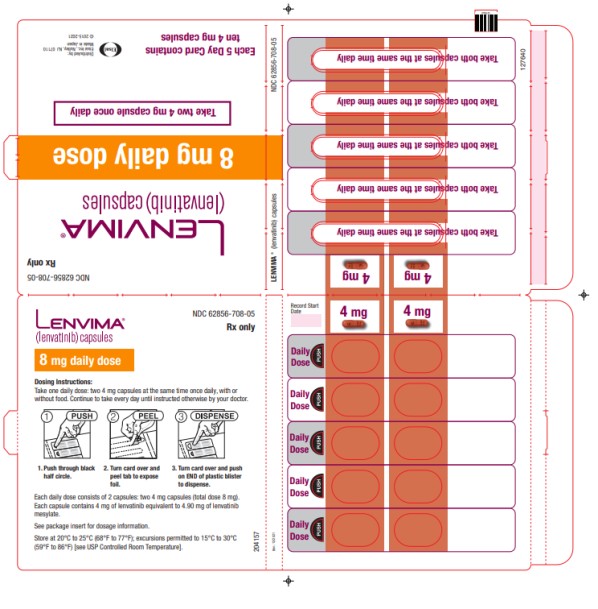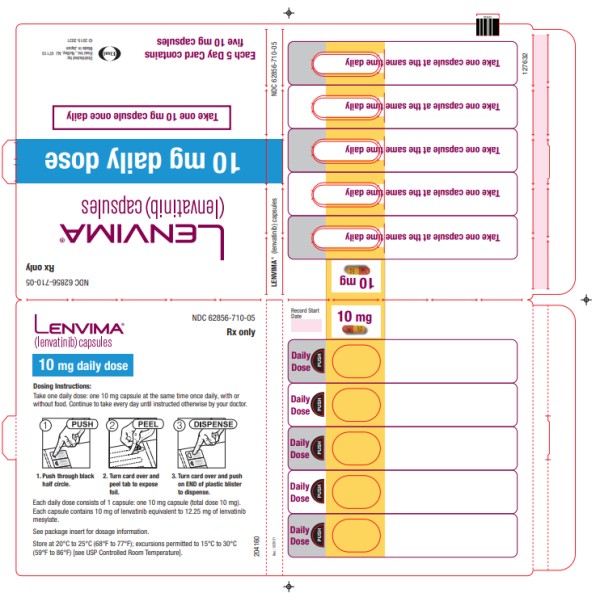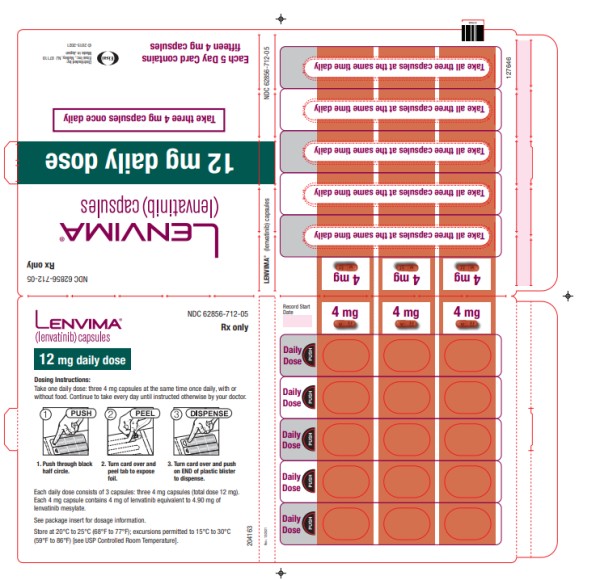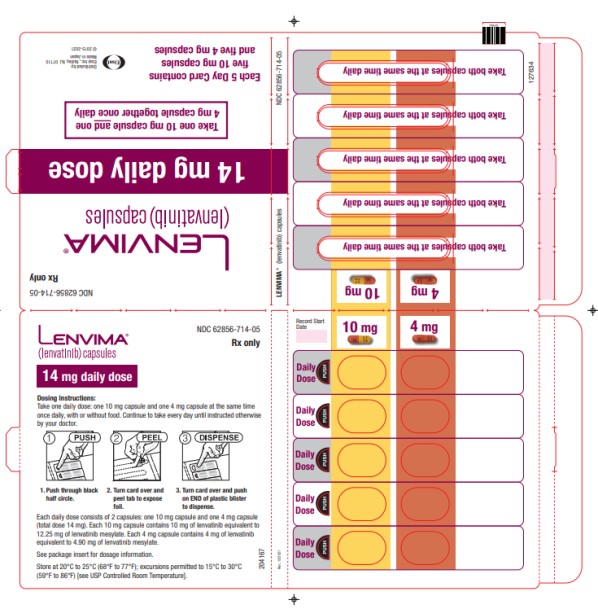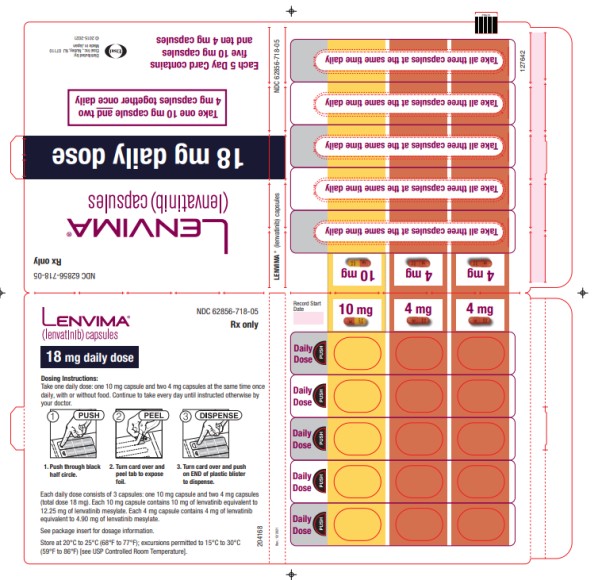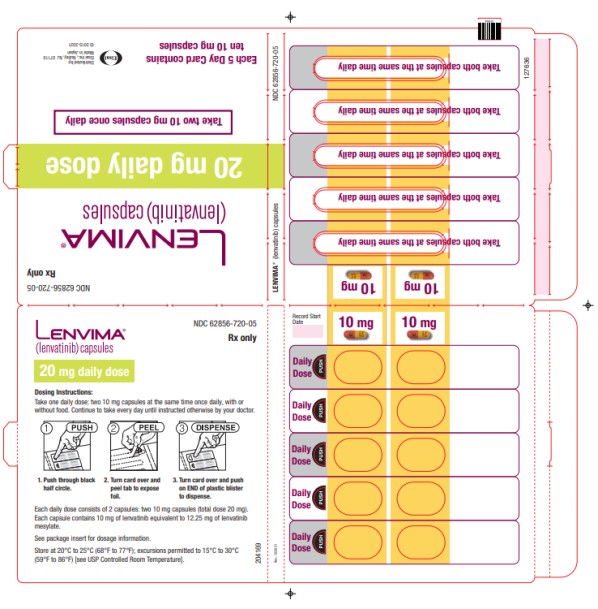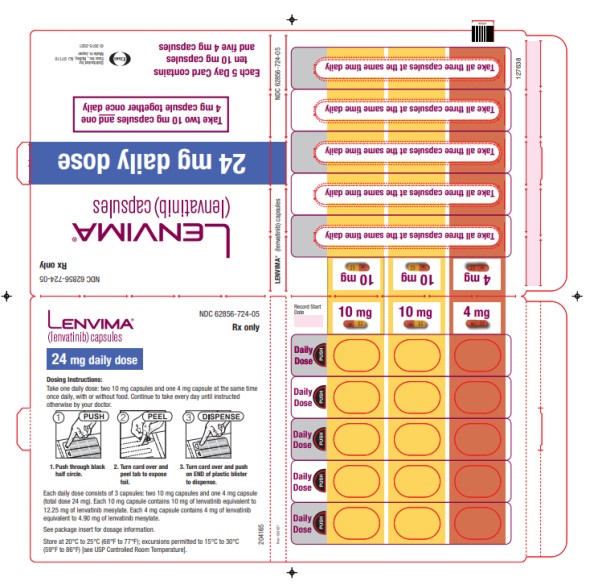 DRUG LABEL: Lenvima
NDC: 62856-704 | Form: CAPSULE
Manufacturer: Eisai Inc.
Category: prescription | Type: HUMAN PRESCRIPTION DRUG LABEL
Date: 20250103

ACTIVE INGREDIENTS: LENVATINIB 4 mg/1 1
INACTIVE INGREDIENTS: CALCIUM CARBONATE; HYDROXYPROPYL CELLULOSE (90000 WAMW); HYDROXYPROPYL CELLULOSE, LOW SUBSTITUTED; MANNITOL; CELLULOSE, MICROCRYSTALLINE; TALC; FERRIC OXIDE RED; FERRIC OXIDE YELLOW; HYPROMELLOSES; TITANIUM DIOXIDE; FERROSOFERRIC OXIDE; POTASSIUM HYDROXIDE; PROPYLENE GLYCOL; SHELLAC

HIGHLIGHTS OF PRESCRIBING INFORMATION

These highlights do not include all the information needed to use
LENVIMA safely and effectively. See full prescribing information for LENVIMA.
LENVIMA® (lenvatinib) capsules, for oral use
Initial U.S. Approval: 2015

RECENT MAJOR CHANGES

Indications and Usage (1.4) | 01/2025
Dosage and Administration (2.1) | 01/2025

1 INDICATIONS AND USAGE

LENVIMA is a kinase inhibitor that is indicated:

Differentiated Thyroid Cancer (DTC)

- For the treatment of adult patients with locally recurrent or metastatic, progressive, radioactive iodine-refractory differentiated thyroid cancer (DTC). (1.1)

Renal Cell Carcinoma (RCC)

- In combination with pembrolizumab, for the first line treatment of adult patients with advanced renal cell carcinoma (RCC). (1.2)
- In combination with everolimus, for the treatment of adult patients with advanced renal cell carcinoma (RCC) following one prior anti-angiogenic therapy. (1.2)

Hepatocellular Carcinoma (HCC)

- For the first-line treatment of patients with unresectable hepatocellular carcinoma (HCC). (1.3)

Endometrial Carcinoma (EC)

- In combination with pembrolizumab, for the treatment of patients with advanced endometrial carcinoma (EC) that is mismatch repair proficient (pMMR) or not microsatellite instability-high (MSI-H), as determined by an FDA-approved test, who have disease progression following prior systemic therapy in any setting and are not candidates for curative surgery or radiation. (1.4, 2.1)

2 DOSAGE AND ADMINISTRATION

Single Agent Therapy:

- DTC: The recommended dosage is 24 mg orally once daily. (2.3)
- HCC: The recommended dosage is based on actual body weight: 12 mg orally once daily for patients greater than or equal to 60 kg or 8 mg orally once daily for patients less than 60 kg. (2.5)

Combination Therapy:

- EC: The recommended dosage is 20 mg orally once daily in combination with pembrolizumab 200 mg administered as an intravenous infusion over 30 minutes every 3 weeks. (2.6)
- RCC: The recommended dosage is:
  - 20 mg orally once daily with pembrolizumab 200 mg administered as an intravenous infusion over 30 minutes every 3 weeks. (2.4)
  - 18 mg orally once daily with everolimus 5 mg orally once daily. (2.4)

Modify the recommended daily dose for certain patients with renal or hepatic impairment. (2.8, 2.9)

3 DOSAGE FORMS AND STRENGTHS

Capsules: 4 mg and 10 mg. (3)

4 CONTRAINDICATIONS

None. (4)

5 WARNINGS AND PRECAUTIONS

- Hypertension: Control blood pressure prior to treatment and monitor during treatment. Withhold for Grade 3 hypertension despite optimal antihypertensive therapy. Discontinue for Grade 4 hypertension. (2.7, 5.1)
- Cardiac Dysfunction: Monitor for clinical symptoms or signs of cardiac dysfunction. Withhold or discontinue for Grade 3 cardiac dysfunction. Discontinue for Grade 4 cardiac dysfunction. (2.7, 5.2)
- Arterial Thromboembolic Events: Discontinue following an arterial thromboembolic event. (2.7, 5.3)
- Hepatotoxicity: Monitor liver function prior to treatment and periodically during treatment. Withhold or discontinue for Grade 3 or 4 hepatotoxicity. Discontinue for hepatic failure. (2.7, 5.4)
- Renal Failure or Impairment: Withhold or discontinue for Grade 3 or 4 renal failure or impairment. (2.7, 5.5)
- Proteinuria: Monitor for proteinuria prior to treatment and periodically during treatment. Withhold for 2 or more grams of proteinuria per 24 hours. Discontinue for nephrotic syndrome. (2.7, 5.6)
- Diarrhea: May be severe and recurrent. Promptly initiate management for severe diarrhea. Withhold or discontinue based on severity. (2.7, 5.7)
- Fistula Formation and Gastrointestinal Perforation: Discontinue in patients who develop Grade 3 or 4 fistula or any Grade gastrointestinal perforation. (2.7, 5.8)
- QT Interval Prolongation: Monitor and correct electrolyte abnormalities. Withhold for QT interval greater than 500 ms or for 60 ms or greater increase in baseline QT interval. (2.7, 5.9)
- Hypocalcemia: Monitor blood calcium levels at least monthly and replace calcium as necessary. Withhold or discontinue based on severity. (2.7, 5.10)
- Reversible Posterior Leukoencephalopathy Syndrome (RPLS): Withhold for RPLS until fully resolved or discontinue. (2.7, 5.11)
- Hemorrhagic Events: Withhold or discontinue based on severity. (2.7, 5.12)
- Impairment of Thyroid Stimulating Hormone Suppression/Thyroid Dysfunction: Monitor thyroid function prior to treatment and monthly during treatment. (5.13)
- Impaired Wound Healing: Withhold LENVIMA for at least 1 week before elective surgery. Do not administer for at least 2 weeks following major surgery and until adequate wound healing. The safety of resumption of LENVIMA after resolution of wound healing complications has not been established. (5.14)
- Osteonecrosis of the Jaw: Consider preventive dentistry prior to treatment with LENVIMA. Avoid invasive dental procedures, if possible, particularly in patients at higher risk. (5.15)
- Embryo-Fetal Toxicity: Can cause fetal harm. Advise females of reproductive potential of the potential risk to a fetus and to use effective contraception. (5.16, 8.1, 8.3)

6 ADVERSE REACTIONS

- In DTC, the most common adverse reactions (incidence ≥30%) for LENVIMA are hypertension, fatigue, diarrhea, arthralgia/myalgia, decreased appetite, decreased weight, nausea, stomatitis, headache, vomiting, proteinuria, palmar-plantar erythrodysesthesia syndrome, abdominal pain, and dysphonia. (6.1)
- In RCC:
  - The most common adverse reactions (incidence ≥20%) for LENVIMA and pembrolizumab are fatigue, diarrhea, musculoskeletal pain, hypothyroidism, hypertension, stomatitis, decreased appetite, rash, nausea, decreased weight, dysphonia, proteinuria, palmar-plantar erythrodysesthesia syndrome, abdominal pain, hemorrhagic events, vomiting, constipation, hepatotoxicity, headache, and acute kidney injury. (6.1)
  - The most common adverse reactions (incidence ≥30%) for LENVIMA and everolimus are diarrhea, fatigue, arthralgia/myalgia, decreased appetite, vomiting, nausea, stomatitis/oral inflammation, hypertension, peripheral edema, cough, abdominal pain, dyspnea, rash, decreased weight, hemorrhagic events, and proteinuria. (6.1)

- In HCC, the most common adverse reactions (incidence ≥20%) for LENVIMA are hypertension, fatigue, diarrhea, decreased appetite, arthralgia/myalgia, decreased weight, abdominal pain, palmar-plantar erythrodysesthesia syndrome, proteinuria, dysphonia, hemorrhagic events, hypothyroidism, and nausea. (6.1)
- In EC, the most common adverse reactions (incidence ≥20%) for LENVIMA and pembrolizumab are hypothyroidism, hypertension, fatigue, diarrhea, musculoskeletal disorders, nausea, decreased appetite, vomiting, stomatitis, decreased weight, abdominal pain, urinary tract infection, proteinuria, constipation, headache, hemorrhagic events, palmar-plantar erythrodysesthesia, dysphonia, and rash. (6.1)

To report SUSPECTED ADVERSE REACTIONS, contact Eisai Inc. at 1-877-873-4724 or FDA at 1-800-FDA-1088 or www.fda.gov/medwatch.

8 USE IN SPECIFIC POPULATIONS

- Lactation: Advise not to breastfeed. (8.2)

FULL PRESCRIBING INFORMATION

1 INDICATIONS AND USAGE

1.1 Differentiated Thyroid Cancer

LENVIMA is indicated for the treatment of adult patients with locally recurrent or metastatic, progressive, radioactive iodine-refractory differentiated thyroid cancer (DTC).

1.2 Renal Cell Carcinoma

LENVIMA, in combination with pembrolizumab, is indicated for the first-line treatment of adult patients with advanced renal cell carcinoma (RCC).

LENVIMA, in combination with everolimus, is indicated for the treatment of adult patients with advanced RCC following one prior anti-angiogenic therapy.

1.3 Hepatocellular Carcinoma

LENVIMA is indicated for the first-line treatment of patients with unresectable hepatocellular carcinoma (HCC).

1.4 Endometrial Carcinoma

LENVIMA, in combination with pembrolizumab, is indicated for the treatment of patients with advanced endometrial carcinoma (EC) that is mismatch repair proficient (pMMR) or not microsatellite instability-high (MSI-H), as determined by an FDA-approved test, who have disease progression following prior systemic therapy in any setting and are not candidates for curative surgery or radiation [see Dosage and Administration (2.1)].

2 DOSAGE AND ADMINISTRATION

2.1 Patient Selection

For the pMMR/not MSI-H advanced endometrial carcinoma indication, select patients for treatment with LENVIMA in combination with pembrolizumab based on MMR or MSI status in tumor specimens [see Clinical Studies (14.4)].

Information on FDA-approved tests for patient selection is available at: http://www.fda.gov/CompanionDiagnostics.

2.2 Important Dosage Information

- Reduce the dose for certain patients with renal or hepatic impairment [see Dosage and Administration (2.8, 2.9)].
- Take LENVIMA once daily, with or without food, at the same time each day [see Clinical Pharmacology (12.3)]. If a dose is missed and cannot be taken within 12 hours, skip that dose and take the next dose at the usual time of administration.

2.3 Recommended Dosage for Differentiated Thyroid Cancer (DTC)

The recommended dosage of LENVIMA is 24 mg orally once daily until disease progression or until unacceptable toxicity.

2.4 Recommended Dosage for Renal Cell Carcinoma (RCC)

First-Line Treatment of Patients with Advanced RCC

The recommended dosage of LENVIMA is 20 mg orally once daily in combination with pembrolizumab 200 mg administered as an intravenous infusion over 30 minutes every 3 weeks until disease progression or until unacceptable toxicity or up to 2 years. After completing 2 years of combination therapy, LENVIMA may be administered as a single agent until disease progression or until unacceptable toxicity.

Refer to the pembrolizumab prescribing information for other pembrolizumab dosing information.

Previously Treated RCC

The recommended dosage of LENVIMA is 18 mg in combination with 5 mg everolimus orally once daily until disease progression or until unacceptable toxicity.

Refer to the everolimus prescribing information for recommended everolimus dosing information.

2.5 Recommended Dosage for Hepatocellular Carcinoma (HCC)

The recommended dosage of LENVIMA is based on actual body weight:

- 12 mg for patients greater than or equal to 60 kg or
- 8 mg for patients less than 60 kg.

Take LENVIMA orally once daily until disease progression or until unacceptable toxicity.

2.6 Recommended Dosage for Endometrial Carcinoma (EC)

The recommended dosage of LENVIMA is 20 mg orally once daily, in combination with pembrolizumab 200 mg administered as an intravenous infusion over 30 minutes every 3 weeks, until unacceptable toxicity or disease progression.

Refer to the pembrolizumab prescribing information for other pembrolizumab dosing information.

2.7 Dosage Modifications for Adverse Reactions

Recommendations for LENVIMA dose interruption, reduction and discontinuation for adverse reactions are listed in Table 1. Table 2 lists the recommended dosage reductions of LENVIMA for adverse reactions.

Table 1: Recommended Dosage Modifications for LENVIMA for Adverse Reactions
Adverse Reaction | Severity a | Dosage Modifications for LENVIMA
Hypertension [see Warnings and Precautions (5.1)] | Grade 3 | - Withhold for Grade 3 that persists despite optimal antihypertensive therapy. - Resume at reduced dose when hypertension is controlled at less than or equal to Grade 2.
 | Grade 4 | - Permanently discontinue.
Cardiac Dysfunction [see Warnings and Precautions (5.2)] | Grade 3 | - Withhold until improves to Grade 0 to 1 or baseline. - Resume at a reduced dose or discontinue depending on the severity and persistence of adverse reaction.
 | Grade 4 | - Permanently discontinue.
Arterial Thromboembolic Event [see Warnings and Precautions (5.3)] | Any Grade | - Permanently discontinue.
Hepatotoxicity [see Warnings and Precautions (5.4)] | Grade 3 or 4 | - Withhold until improves to Grade 0 to 1 or baseline. - Either resume at a reduced dose or discontinue depending on severity and persistence of hepatotoxicity. - Permanently discontinue for hepatic failure.
Renal Failure or Impairment [see Warnings and Precautions (5.5)] | Grade 3 or 4 | - Withhold until improves to Grade 0 to 1 or baseline. - Resume at a reduced dose or discontinue depending on severity and persistence of renal impairment.
Proteinuria [see Warnings and Precautions (5.6)] | 2 g or greater proteinuria in 24 hours | - Withhold until less than or equal to 2 grams of proteinuria per 24 hours. - Resume at a reduced dose. - Permanently discontinue for nephrotic syndrome.
Gastrointestinal Perforation [see Warnings and Precautions (5.8)] | Any Grade | - Permanently discontinue.
Fistula Formation [see Warnings and Precautions (5.8)] | Grade 3 or 4 | - Permanently discontinue.
QT Prolongation [see Warnings and Precautions (5.9)] | Greater than 500 ms or greater than 60 ms increase from baseline | - Withhold until improves to less than or equal to 480 ms or baseline. - Resume at a reduced dose.
Reversible Posterior Leukoencephalopathy Syndrome [see Warnings and Precautions (5.11)] | Any Grade | - Withhold until fully resolved. - Resume at a reduced dose or discontinue depending on severity and persistence of neurologic symptoms.
Other Adverse Reactions [see Warnings and Precautions (5.7, 5.10, 5.12)] | Persistent or intolerable Grade 2 or 3 adverse reaction Grade 4 laboratory abnormality | - Withhold until improves to Grade 0 to 1 or baseline. - Resume at reduced dose.
 | Grade 4 adverse reaction | - Permanently discontinue.
a. National Cancer Institute Common Terminology Criteria for Adverse Events, version 4.0.

Table 2: Recommended Dosage Reductions of LENVIMA for Adverse Reactions
Indication | First Dosage Reduction To | Second Dosage Reduction To | Third Dosage Reduction To
DTC | 20 mg once daily | 14 mg once daily | 10 mg once daily
RCC | 14 mg once daily | 10 mg once daily | 8 mg once daily
Endometrial Carcinoma | 14 mg once daily | 10 mg once daily | 8 mg once daily
HCC
- Actual weight 60 kg or greater | 8 mg once daily | 4 mg once daily | 4 mg every other day
- Actual weight less than 60 kg | 4 mg once daily | 4 mg every other day | Discontinue

Recommended Dose Modifications for Adverse Reactions for LENVIMA in Combination with Pembrolizumab

When administering LENVIMA in combination with pembrolizumab, modify the dosage of one or both drugs as appropriate. Withhold, dose reduce, or discontinue LENVIMA as shown in Table 1. Refer to pembrolizumab prescribing information for additional dose modification information.

Recommended Dose Modifications for Adverse Reactions for LENVIMA in Combination with Everolimus

When administering LENVIMA in combination with everolimus, withhold or reduce the LENVIMA dose first and then the everolimus dose for adverse reactions of both LENVIMA and everolimus. Refer to the everolimus prescribing information for additional dose modification information.

2.8 Dosage Modifications for Severe Renal Impairment

The recommended dosage of LENVIMA for patients with DTC, RCC, or endometrial carcinoma and severe renal impairment (creatinine clearance less than 30 mL/min calculated by Cockcroft-Gault equation using actual body weight) is [see Warnings and Precautions (5.5), Use in Specific Populations (8.6)]:

- Differentiated thyroid cancer: 14 mg orally once daily
- Renal cell carcinoma: 10 mg orally once daily
- Endometrial carcinoma: 10 mg orally once daily

2.9 Dosage Modifications for Severe Hepatic Impairment

The recommended dosage of LENVIMA for patients with DTC, RCC, or endometrial carcinoma and severe hepatic impairment (Child-Pugh C) is [see Warnings and Precautions (5.4), Use in Specific Populations (8.7)]:

- Differentiated thyroid cancer: 14 mg taken orally once daily
- Renal cell carcinoma: 10 mg taken orally once daily
- Endometrial carcinoma: 10 mg orally once daily

2.10 Capsule Administration and Preparation of Suspension for Administration

Administration

Oral: Capsule or Suspension

Capsule

- Swallow LENVIMA capsules whole at the same time each day with or without food [see Clinical Pharmacology (12.3)]. Do not crush or chew the LENVIMA capsules.

Suspension

- Prepare [see Preparation below] oral suspension with water or apple juice and administer at the same time each day with or without food [see Clinical Pharmacology (12.3)].

Feeding Tube Administration

Suspension

- Prepare [see Preparation below] suspension for feeding tube administration with water and administer at the same time each day with or without food [see Clinical Pharmacology (12.3)].

Preparation of Suspension

- Place the required number of capsules, up to a maximum of 5, in a small container (approximately 20 mL capacity) or syringe (20 mL). Do not break or crush capsules.
- Add 3 mL of liquid to the container or syringe. Wait 10 minutes for the capsule shell (outer surface) to disintegrate, then stir or shake the mixture for 3 minutes until capsules are fully disintegrated and administer the entire contents.
- Next, add an additional 2 mL of liquid to the container or syringe using a second syringe or dropper, swirl or shake and administer. Repeat this step at least once and until there is no visible residue to ensure all of the medication is taken.
- If 6 capsules are required for a dose, follow these instructions using 3 capsules at a time.

If LENVIMA suspension is not used at the time of preparation, LENVIMA suspension may be stored in a refrigerator at 36ºF to 46ºF (2ºC to 8ºC) for a maximum of 24 hours in a covered container. If not administered within 24 hours, the suspension should be discarded.

Note: Compatibility has been confirmed for polypropylene syringes and for feeding tubes of at least 5 French diameter (polyvinyl chloride or polyurethane tube) and at least 6 French diameter (silicone tube).

3 DOSAGE FORMS AND STRENGTHS

Capsules:

- 4 mg: yellowish-red body and yellowish-red cap, marked in black ink with “Є” on cap and “LENV 4 mg” on body.
- 10 mg: yellow body and yellowish-red cap, marked in black ink with “Є” on cap and “LENV 10 mg” on body.

4 CONTRAINDICATIONS

None.

5 WARNINGS AND PRECAUTIONS

5.1 Hypertension

Hypertension occurred in 73% of patients in SELECT (DTC) receiving LENVIMA 24 mg orally once daily and in 45% of patients in REFLECT (HCC) receiving LENVIMA 8 mg or 12 mg orally once daily. The median time to onset of new or worsening hypertension was 16 days in SELECT and 26 days in REFLECT. Grade 3 hypertension occurred in 44% of patients in SELECT and in 24% in REFLECT. Grade 4 hypertension occurred <1% in SELECT and Grade 4 hypertension was not reported in REFLECT.

In patients receiving LENVIMA 18 mg orally once daily with everolimus in Study 205 (RCC), hypertension was reported in 42% of patients and the median time to onset of new or worsening hypertension was 35 days. Grade 3 hypertension occurred in 13% of patients. Systolic blood pressure ≥160 mmHg occurred in 29% of patients and diastolic blood pressure ≥100 mmHg occurred in 21% [see Adverse Reactions (6.1)].

Serious complications of poorly controlled hypertension have been reported.

Control blood pressure prior to initiating LENVIMA. Monitor blood pressure after 1 week, then every 2 weeks for the first 2 months, and then at least monthly thereafter during treatment. Withhold and resume at a reduced dose when hypertension is controlled or permanently discontinue LENVIMA based on severity [see Dosage and Administration (2.7)].

5.2 Cardiac Dysfunction

Serious and fatal cardiac dysfunction can occur with LENVIMA. Across clinical trials in 799 patients with DTC, RCC or HCC, Grade 3 or higher cardiac dysfunction (including cardiomyopathy, left or right ventricular dysfunction, congestive heart failure, cardiac failure, ventricular hypokinesia, or decrease in left or right ventricular ejection fraction of more than 20% from baseline) occurred in 3% of LENVIMA-treated patients.

Monitor patients for clinical symptoms or signs of cardiac dysfunction. Withhold and resume at a reduced dose upon recovery or permanently discontinue LENVIMA based on severity [see Dosage and Administration (2.7)].

5.3 Arterial Thromboembolic Events

Among patients receiving LENVIMA or LENVIMA with everolimus, arterial thromboembolic events of any severity occurred in 2% of patients in Study 205 (RCC), 2% of patients in REFLECT (HCC) and 5% of patients in SELECT (DTC). Grade 3 to 5 arterial thromboembolic events ranged from 2% to 3% across all clinical trials [see Adverse Reactions (6.1)].

Among patients receiving LENVIMA with pembrolizumab, arterial thrombotic events of any severity occurred in 5% of patients in CLEAR, including myocardial infarction (3.4%) and cerebrovascular accident (2.3%).

Permanently discontinue LENVIMA following an arterial thrombotic event [see Dosage and Administration (2.7)]. The safety of resuming LENVIMA after an arterial thromboembolic event has not been established and LENVIMA has not been studied in patients who have had an arterial thromboembolic event within the previous 6 months.

5.4 Hepatotoxicity

Across clinical studies enrolling 1327 LENVIMA-treated patients with malignancies other than HCC, serious hepatic adverse reactions occurred in 1.4% of patients. Fatal events, including hepatic failure, acute hepatitis and hepatorenal syndrome, occurred in 0.5% of patients.

In REFLECT (HCC), hepatic encephalopathy (including hepatic encephalopathy, encephalopathy, metabolic encephalopathy, and hepatic coma) occurred in 8% of LENVIMA-treated patients and 3% of sorafenib-treated patients. Grade 3 to 5 hepatic encephalopathy occurred in 5% of LENVIMA-treated patients and 2% of sorafenib-treated patients. Grade 3 to 5 hepatic failure occurred in 3% of LENVIMA-treated patients and 3% of sorafenib-treated patients. Two percent of patients discontinued LENVIMA and 0.2% discontinued sorafenib due to hepatic encephalopathy and 1% of patients discontinued LENVIMA or sorafenib due to hepatic failure [see Adverse Reactions (6.1)].

Monitor liver function prior to initiating LENVIMA, then every 2 weeks for the first 2 months, and at least monthly thereafter during treatment. Monitor patients with HCC closely for signs of hepatic failure, including hepatic encephalopathy. Withhold and resume at a reduced dose upon recovery or permanently discontinue LENVIMA based on severity [see Dosage and Administration (2.7)].

5.5 Renal Failure or Impairment

Serious including fatal renal failure or impairment can occur with LENVIMA. Renal impairment occurred in 14% of patients receiving LENVIMA in SELECT (DTC) and in 7% of patients receiving LENVIMA in REFLECT (HCC). Grade 3 to 5 renal failure or impairment occurred in 3% (DTC) and 2% (HCC) of patients, including 1 fatality in each study.

In Study 205 (RCC), renal impairment or renal failure occurred in 18% of patients receiving LENVIMA with everolimus, including Grade 3 in 10% of patients [see Adverse Reactions (6.1)].

Initiate prompt management of diarrhea or dehydration/hypovolemia. Withhold and resume at a reduced dose upon recovery or permanently discontinue LENVIMA for renal failure or impairment based on severity [see Dosage and Administration (2.7)].

5.6 Proteinuria

Proteinuria occurred in 34% of LENVIMA-treated patients in SELECT (DTC) and in 26% of LENVIMA-treated patients in REFLECT (HCC). Grade 3 proteinuria occurred in 11% and 6% in SELECT and REFLECT, respectively. In Study 205 (RCC), proteinuria occurred in 31% of patients receiving LENVIMA with everolimus and 14% of patients receiving everolimus. Grade 3 proteinuria occurred in 8% of patients receiving LENVIMA with everolimus compared to 2% of patients receiving everolimus [see Adverse Reactions (6.1)].

Monitor for proteinuria prior to initiating LENVIMA and periodically during treatment. If urine dipstick proteinuria greater than or equal to 2+ is detected, obtain a 24-hour urine protein. Withhold and resume at a reduced dose upon recovery or permanently discontinue LENVIMA based on severity [see Dosage and Administration (2.7)].

5.7 Diarrhea

Of the 737 patients treated with LENVIMA in SELECT (DTC) and REFLECT (HCC), diarrhea occurred in 49% of patients, including Grade 3 in 6%.

In Study 205 (RCC), diarrhea occurred in 81% of patients receiving LENVIMA with everolimus, including Grade 3 in 19%. Diarrhea was the most frequent cause of dose interruption/reduction and diarrhea recurred despite dose reduction [see Adverse Reactions (6.1)].

Promptly initiate management of diarrhea. Withhold and resume at a reduced dose upon recovery or permanently discontinue LENVIMA based on severity [see Dosage and Administration (2.7)].

5.8 Fistula Formation and Gastrointestinal Perforation

Of 799 patients treated with LENVIMA or LENVIMA with everolimus in SELECT (DTC), Study 205 (RCC) and REFLECT (HCC), fistula or gastrointestinal perforation occurred in 2%.

Permanently discontinue LENVIMA in patients who develop gastrointestinal perforation of any severity or Grade 3 or 4 fistula [see Dosage and Administration (2.7)].

5.9 QT Interval Prolongation

In SELECT (DTC), QT/QTc interval prolongation occurred in 9% of LENVIMA-treated patients and QT interval prolongation of >500 ms occurred in 2%. In Study 205 (RCC), QTc interval increases of >60 ms occurred in 11% of patients receiving LENVIMA with everolimus and QTc interval >500 ms occurred in 6%. In REFLECT (HCC), QTc interval increases of >60 ms occurred in 8% of LENVIMA-treated patients and QTc interval >500 ms occurred in 2%.

Monitor and correct electrolyte abnormalities at baseline and periodically during treatment. Monitor electrocardiograms in patients with congenital long QT syndrome, congestive heart failure, bradyarrhythmias, or those who are taking drugs known to prolong the QT interval, including Class Ia and III antiarrhythmics. Withhold and resume at reduced dose of LENVIMA upon recovery based on severity [see Dosage and Administration (2.7)].

5.10 Hypocalcemia

In SELECT (DTC), Grade 3 to 4 hypocalcemia occurred in 9% of patients receiving LENVIMA. In 65% of cases, hypocalcemia improved or resolved following calcium supplementation, with or without dose interruption or dose reduction.

In Study 205 (RCC), Grade 3 to 4 hypocalcemia occurred in 6% of patients treated with LENVIMA with everolimus. In REFLECT (HCC), Grade 3 hypocalcemia occurred in 0.8% of LENVIMA-treated patients [see Adverse Reactions (6.1)].

Monitor blood calcium levels at least monthly and replace calcium as necessary during treatment. Withhold and resume at reduced dose upon recovery or permanently discontinue LENVIMA depending on severity [see Dosage and Administration (2.7)].

5.11 Reversible Posterior Leukoencephalopathy Syndrome

Across clinical studies of 1823 patients who received LENVIMA as a single agent [see Adverse Reactions (6.1)], reversible posterior leukoencephalopathy syndrome (RPLS) occurred in 0.3%.

Confirm the diagnosis of RPLS with magnetic resonance imaging. Withhold and resume at a reduced dose upon recovery or permanently discontinue LENVIMA depending on severity and persistence of neurologic symptoms [see Dosage and Administration (2.7)].

5.12 Hemorrhagic Events

Serious including fatal hemorrhagic events can occur with LENVIMA. Across SELECT (DTC), Study 205 (RCC) and REFLECT (HCC), hemorrhagic events of any grade occurred in 29% of the 799 patients treated with LENVIMA as a single agent or in combination with everolimus. The most frequently reported hemorrhagic events (all grades and occurring in at least 5% of patients) were epistaxis and hematuria.

In SELECT, Grade 3 to 5 hemorrhage occurred in 2% of patients receiving LENVIMA, including 1 fatal intracranial hemorrhage among 16 patients who received LENVIMA and had CNS metastases at baseline. In Study 205, Grade 3 to 5 hemorrhage occurred in 8% of patients receiving LENVIMA with everolimus, including 1 fatal cerebral hemorrhage. In REFLECT, Grade 3 to 5 hemorrhage occurred in 5% of patients receiving LENVIMA, including 7 fatal hemorrhagic events [see Adverse Reactions (6.1)].

Serious tumor related bleeds, including fatal hemorrhagic events, occurred in patients treated with LENVIMA in clinical trials and in the post-marketing setting. In post-marketing surveillance, serious and fatal carotid artery hemorrhages were seen more frequently in patients with anaplastic thyroid carcinoma (ATC) than in other tumor types. The safety and effectiveness of LENVIMA in patients with ATC have not been demonstrated in clinical trials.

Consider the risk of severe or fatal hemorrhage associated with tumor invasion or infiltration of major blood vessels (e.g. carotid artery). Withhold and resume at reduced dose upon recovery or permanently discontinue LENVIMA based on the severity [see Dosage and Administration (2.7)].

5.13 Impairment of Thyroid Stimulating Hormone Suppression/Thyroid Dysfunction

LENVIMA impairs exogenous thyroid suppression. In SELECT (DTC), 88% of all patients had a baseline thyroid stimulating hormone (TSH) level ≤0.5 mU/L. In those patients with a normal TSH at baseline, elevation of TSH level >0.5 mU/L was observed post baseline in 57% of LENVIMA-treated patients.

Grade 1 or 2 hypothyroidism occurred in 24% of patients receiving LENVIMA with everolimus in Study 205 (RCC) and in 21% of patients receiving LENVIMA in REFLECT (HCC). In those patients with a normal or low TSH at baseline, an elevation of TSH was observed post baseline in 70% of patients receiving LENVIMA in REFLECT and 60% of patients receiving LENVIMA with everolimus in Study 205 [see Adverse Reactions (6.1)].

Monitor thyroid function prior to initiating LENVIMA and at least monthly during treatment. Treat hypothyroidism according to standard medical practice.

5.14 Impaired Wound Healing

Impaired wound healing has been reported in patients who received LENVIMA [see Adverse Reactions (6.2)].

Withhold LENVIMA for at least 1 week prior to elective surgery. Do not administer for at least 2 weeks following major surgery and until adequate wound healing. The safety of resumption of LENVIMA after resolution of wound healing complications has not been established.

5.15 Osteonecrosis of the Jaw (ONJ)

Osteonecrosis of the Jaw (ONJ) has been reported in patients receiving LENVIMA [see Adverse Reactions (6.1)]. Concomitant exposure to other risk factors, such as bisphosphonates, denosumab, dental disease or invasive dental procedures, may increase the risk of ONJ.

Perform an oral examination prior to treatment with LENVIMA and periodically during LENVIMA treatment. Advise patients regarding good oral hygiene practices. Avoid invasive dental procedures, if possible, while on LENVIMA treatment, particularly in patients at higher risk. Withhold LENVIMA for at least 1 week prior to scheduled dental surgery or invasive dental procedures, if possible. For patients requiring invasive dental procedures, discontinuation of bisphosphonate treatment may reduce the risk of ONJ. Withhold LENVIMA if ONJ develops and restart based on clinical judgement of adequate resolution.

5.16 Embryo-Fetal Toxicity

Based on its mechanism of action and data from animal reproduction studies, LENVIMA can cause fetal harm when administered to a pregnant woman. In animal reproduction studies, oral administration of lenvatinib during organogenesis at doses below the recommended clinical doses resulted in embryotoxicity, fetotoxicity, and teratogenicity in rats and rabbits.

Advise pregnant women of the potential risk to a fetus. Advise females of reproductive potential to use effective contraception during treatment with LENVIMA and for 30 days after the last dose [see Use in Specific Populations (8.1, 8.3)].

6 ADVERSE REACTIONS

The following adverse reactions are discussed elsewhere in the labeling:

- Hypertension [see Warnings and Precautions (5.1)]
- Cardiac Dysfunction [see Warnings and Precautions (5.2)]
- Arterial Thromboembolic Events [see Warnings and Precautions (5.3)]
- Hepatotoxicity [see Warnings and Precautions (5.4)]
- Renal Failure and Impairment [see Warnings and Precautions (5.5)]
- Proteinuria [see Warnings and Precautions (5.6)]
- Diarrhea [see Warnings and Precautions (5.7)]
- Fistula Formation and Gastrointestinal Perforation [see Warnings and Precautions (5.8)]
- QT Interval Prolongation [see Warnings and Precautions (5.9)]
- Hypocalcemia [see Warnings and Precautions (5.10)]
- Reversible Posterior Leukoencephalopathy Syndrome [see Warnings and Precautions (5.11)]
- Hemorrhagic Events [see Warnings and Precautions (5.12)]
- Impairment of Thyroid Stimulating Hormone Suppression/Thyroid Dysfunction [see Warnings and Precautions (5.13)]
- Impaired Wound Healing [see Warnings and Precautions (5.14)]
- Osteonecrosis of the Jaw (ONJ) [see Warnings and Precautions (5.15)]

6.1 Clinical Trials Experience

Because clinical trials are conducted under widely varying conditions, adverse reaction rates observed in the clinical trials of a drug cannot be directly compared to rates in the clinical trials of another drug and may not reflect the rates observed in practice.

The data in the Warnings and Precautions reflect exposure to LENVIMA as a single agent in 261 patients with DTC (SELECT) and 476 patients with HCC (REFLECT), LENVIMA with pembrolizumab in 406 patients with endometrial carcinoma (Study 309), LENVIMA with everolimus in 62 patients with RCC (Study 205), and LENVIMA with pembrolizumab in 352 patients with RCC (CLEAR). Safety data obtained in 1823 patients with advanced solid tumors who received LENVIMA as a single agent across multiple clinical studies was used to further characterize the risks of serious adverse reactions. Among the 1823 patients who received LENVIMA as a single agent, the median age was 61 years (20 to 89 years), the dose range was 0.2 mg to 32 mg daily, and the median duration of exposure was 5.6 months.

The data below reflect exposure to LENVIMA in 1557 patients enrolled in randomized, active-controlled trials (REFLECT; Study 205; CLEAR; Study 309), and a randomized, placebo-controlled trial (SELECT). The median duration of exposure to LENVIMA across these five studies ranged from 6 to 16 months. The demographic and exposure data for each clinical trial population are described in the subsections below.

Differentiated Thyroid Cancer

The safety of LENVIMA was evaluated in SELECT, in which patients with radioactive iodine-refractory differentiated thyroid cancer were randomized (2:1) to LENVIMA (n=261) or placebo (n=131) [see Clinical Studies (14.1)]. The median treatment duration was 16.1 months for LENVIMA. Among 261 patients who received LENVIMA, median age was 64 years, 52% were females, 80% were White, 18% were Asian, and 2% were Black; and 4% were Hispanic/Latino.

The most common adverse reactions observed in LENVIMA-treated patients (≥30%) were, in order of decreasing frequency, hypertension, fatigue, diarrhea, arthralgia/myalgia, decreased appetite, decreased weight, nausea, stomatitis, headache, vomiting, proteinuria, palmar-plantar erythrodysesthesia (PPE) syndrome, abdominal pain, and dysphonia. The most common serious adverse reactions (at least 2%) were pneumonia (4%), hypertension (3%), and dehydration (3%).

Adverse reactions led to dose reductions in 68% of patients receiving LENVIMA; 18% of patients discontinued LENVIMA for adverse reactions. The most common adverse reactions (at least 10%) resulting in dose reductions of LENVIMA were hypertension (13%), proteinuria (11%), decreased appetite (10%), and diarrhea (10%); the most common adverse reactions (at least 1%) resulting in discontinuation of LENVIMA were hypertension (1%) and asthenia (1%).

Table 3 presents adverse reactions occurring at a higher rate in LENVIMA-treated patients than patients receiving placebo in the double-blind phase of the study.

Table 3: Adverse Reactions Occurring in Patients with a Between-Group Difference of ≥5% in All Grades or ≥2% in Grades 3 and 4 in SELECT (DTC)
Adverse Reaction | LENVIMA 24 mg N=261 |  | Placebo N=131
 | All Grades (%) | Grades 3-4 (%) | All Grades (%) | Grades 3-4 (%)
Vascular
Hypertensiona | 73 | 44 | 16 | 4
Hypotension | 9 | 2 | 2 | 0
Gastrointestinal
Diarrhea | 67 | 9 | 17 | 0
Nausea | 47 | 2 | 25 | 1
Stomatitisb | 41 | 5 | 8 | 0
Vomiting | 36 | 2 | 15 | 0
Abdominal painc | 31 | 2 | 11 | 1
Constipation | 29 | 0.4 | 15 | 1
Oral paind | 25 | 1 | 2 | 0
Dry mouth | 17 | 0.4 | 8 | 0
Dyspepsia | 13 | 0.4 | 4 | 0
General
Fatiguee | 67 | 11 | 35 | 4
Edema peripheral | 21 | 0.4 | 8 | 0
Musculoskeletal and Connective Tissue
Arthralgia/Myalgiaf | 62 | 5 | 28 | 3
Metabolism and Nutrition
Decreased appetite | 54 | 7 | 18 | 1
Decreased weight | 51 | 13 | 15 | 1
Dehydration | 9 | 2 | 2 | 1
Nervous System
Headache | 38 | 3 | 11 | 1
Dysgeusia | 18 | 0 | 3 | 0
Dizziness | 15 | 0.4 | 9 | 0
Renal and Urinary
Proteinuria | 34 | 11 | 3 | 0
Skin and Subcutaneous Tissue
Palmar-plantar erythrodysesthesia | 32 | 3 | 1 | 0
Rashg | 21 | 0.4 | 3 | 0
Alopecia | 12 | 0 | 5 | 0
Hyperkeratosis | 7 | 0 | 2 | 0
Respiratory, Thoracic and Mediastinal
Dysphonia | 31 | 1 | 5 | 0
Cough | 24 | 0 | 18 | 0
Epistaxis | 12 | 0 | 1 | 0
Psychiatric
Insomnia | 12 | 0 | 3 | 0
Infections
Urinary tract infection | 11 | 1 | 5 | 0
Dental and oral infectionsh | 10 | 1 | 1 | 0
Cardiac
Electrocardiogram QT prolonged | 9 | 2 | 2 | 0
a. Includes hypertension, hypertensive crisis, increased blood pressure diastolic, and increased blood pressure
b. Includes aphthous stomatitis, stomatitis, glossitis, mouth ulceration, and mucosal inflammation
c. Includes abdominal discomfort, abdominal pain, lower abdominal pain, upper abdominal pain, abdominal tenderness, epigastric discomfort, and gastrointestinal pain
d. Includes oral pain, glossodynia, and oropharyngeal pain
e. Includes asthenia, fatigue, and malaise
f. Includes musculoskeletal pain, back pain, pain in extremity, arthralgia, and myalgia
g. Includes macular rash, maculo-papular rash, generalized rash, and rash
h. Includes gingivitis, oral infection, parotitis, pericoronitis, periodontitis, sialoadenitis, tooth abscess, and tooth infection

Clinically important adverse reactions occurring more frequently in LENVIMA-treated patients than patients receiving placebo, but with an incidence of <5% were pulmonary embolism (3%, including fatal reports vs 2%, respectively) and osteonecrosis of the jaw (0.4% vs 0%, respectively).

Laboratory abnormalities with a difference of ≥2% in Grade 3 – 4 events and at a higher incidence in the LENVIMA arm are presented in Table 4.

Table 4: Laboratory Abnormalities with a Difference of ≥2% in Grade 3 - 4 Events and at a Higher Incidence in the LENVIMA Arma, b in SELECT (DTC)
Laboratory Abnormality | LENVIMA 24 mg | Placebo
 | Grades 3-4 (%) | Grades 3-4 (%)
Chemistry
Hypocalcemia | 9 | 2
Hypokalemia | 6 | 1
Increased aspartate aminotransferase (AST) | 5 | 0
Increased alanine aminotransferase (ALT) | 4 | 0
Increased lipase | 4 | 1
Increased creatinine | 3 | 0
Hematology
Thrombocytopenia | 2 | 0
a. With at least 1 grade increase from baseline
b. Laboratory Abnormality percentage is based on the number of patients who had both baseline and at least one post baseline laboratory measurement for each parameter. LENVIMA (n = 253 to 258), Placebo (n = 129 to 131)

The following laboratory abnormalities (all Grades) occurred in >5% of LENVIMA-treated patients and at a rate that was two-fold or higher than in patients who received placebo: hypoalbuminemia, increased alkaline phosphatase, hypomagnesemia, hypoglycemia, hyperbilirubinemia, hypercalcemia, hypercholesterolemia, increased serum amylase, and hyperkalemia.

First-Line Treatment of Renal Cell Carcinoma in Combination with Pembrolizumab (CLEAR)

The safety of LENVIMA in combination with pembrolizumab was investigated in CLEAR [see Clinical Studies (14.2)]. Patients received LENVIMA 20 mg orally once daily in combination with pembrolizumab 200 mg intravenously every 3 weeks (n=352), or LENVIMA 18 mg orally once daily in combination with everolimus 5 mg orally once daily (n=355), or sunitinib 50 mg orally once daily for 4 weeks then off treatment for 2 weeks (n=340). The median duration of exposure to the combination therapy of LENVIMA and pembrolizumab was 17 months (range: 0.1 to 39).

Fatal adverse reactions occurred in 4.3% of patients receiving LENVIMA in combination with pembrolizumab, including cardio-respiratory arrest (0.9%), sepsis (0.9%), and one case (0.3%) each of arrhythmia, autoimmune hepatitis, dyspnea, hypertensive crisis, increased blood creatinine, multiple organ dysfunction syndrome, myasthenic syndrome, myocarditis, nephritis, pneumonitis, ruptured aneurysm and subarachnoid hemorrhage.

Serious adverse reactions occurred in 51% of patients receiving LENVIMA and pembrolizumab. Serious adverse reactions in ≥2% of patients were hemorrhagic events (5%), diarrhea (4%), hypertension (3%), myocardial infarction (3%), pneumonitis (3%), vomiting (3%), acute kidney injury (2%), adrenal insufficiency (2%), dyspnea (2%), and pneumonia (2%).

Permanent discontinuation of LENVIMA, pembrolizumab, or both due to an adverse reaction occurred in 37% of patients; 26% LENVIMA only, 29% pembrolizumab only, and 13% both drugs. The most common adverse reactions (≥2%) leading to permanent discontinuation of LENVIMA, pembrolizumab, or both were pneumonitis (3%), myocardial infarction (3%), hepatotoxicity (3%), acute kidney injury (3%), rash (3%), and diarrhea (2%).

Dose interruptions of LENVIMA, pembrolizumab, or both due to an adverse reaction occurred in 78% of patients receiving LENVIMA in combination with pembrolizumab. LENVIMA was interrupted in 73% of patients and both drugs were interrupted in 39% of patients. LENVIMA was dose reduced in 69% of patients. The most common adverse reactions (≥5%) resulting in dose reduction or interruption of LENVIMA were diarrhea (26%), fatigue (18%), hypertension (17%), proteinuria (13%), decreased appetite (12%), palmar-plantar erythrodysesthesia (11%), nausea (9%), stomatitis (9%), musculoskeletal pain (8%), rash (8%), increased lipase (7%), abdominal pain (6%), and vomiting (6%), increased ALT (5%), and increased amylase (5%).

Tables 5 and 6 summarize the adverse reactions and laboratory abnormalities, respectively, that occurred in ≥20% of patients treated with LENVIMA and pembrolizumab in CLEAR.

Table 5: Adverse Reactions in ≥20% of Patients on LENVIMA plus Pembrolizumab in CLEAR (RCC)
 | LENVIMA 20 mg in combination with Pembrolizumab 200mg N=352 |  | Sunitinib 50 mg N=340
Adverse Reactions | All Grades (%) | Grade 3-4 (%) | All Grades (%) | Grade 3-4 (%)
General
Fatiguea | 63 | 9 | 56 | 8
Gastrointestinal
Diarrheab | 62 | 10 | 50 | 6
Stomatitisc | 43 | 2 | 43 | 2
Nausea | 36 | 3 | 33 | 1
Abdominal paind | 27 | 2 | 18 | 1
Vomiting | 26 | 3 | 20 | 1
Constipation | 25 | 1 | 19 | 0
Musculoskeletal and connective tissue
Musculoskeletal paine | 58 | 4 | 41 | 3
Endocrine
Hypothyroidismf | 57 | 1 | 32 | 0
Vascular
Hypertensiong | 56 | 29 | 43 | 20
Hemorrhagic eventsh | 27 | 5 | 26 | 4
Metabolism
Decreased appetitei | 41 | 4 | 31 | 1
Skin and subcutaneous tissue
Rashj | 37 | 5 | 17 | 1
Palmar-plantar erythrodysaesthesia syndromek | 29 | 4 | 38 | 4
Respiratory, thoracic, and mediastinal
Dysphonia | 30 | 0 | 4 | 0
Renal and urinary
Proteinurial | 30 | 8 | 13 | 3
Acute kidney injurym | 21 | 5 | 16 | 2
Investigations
Weight decreased | 30 | 8 | 9 | 0
Hepatobiliary
Hepatotoxicityn | 25 | 9 | 21 | 5
Nervous system
Headache | 23 | 1 | 16 | 1
a. Includes asthenia, fatigue, lethargy and malaise
b. Includes diarrhea and gastroenteritis
c. Includes aphthous ulcer, gingival pain, glossitis, glossodynia, mouth ulceration, mucosal inflammation, oral discomfort, oral mucosal blistering, oral pain, oropharyngeal pain, pharyngeal inflammation, and stomatitis
d. Includes abdominal discomfort, abdominal pain, abdominal rigidity, abdominal tenderness, epigastric discomfort, lower abdominal pain, and upper abdominal pain
e. Includes arthralgia, arthritis, back pain, bone pain, breast pain, musculoskeletal chest pain, musculoskeletal discomfort, musculoskeletal pain, musculoskeletal stiffness, myalgia, neck pain, non-cardiac chest pain, pain in extremity, and pain in jaw
f. Includes hypothyroidism, increased blood thyroid stimulating hormone and secondary hypothyroidism
g. Includes essential hypertension, increased blood pressure, increased diastolic blood pressure, hypertension, hypertensive crisis, hypertensive retinopathy, and labile blood pressure
h. Includes all hemorrhage terms. Hemorrhage terms that occurred in 1 or more subjects in either treatment group include: Anal hemorrhage, aneurysm ruptured, blood blister, blood loss anemia, blood urine present, catheter site hematoma, cerebral microhemorrhage, conjunctival hemorrhage, contusion, diarrhea hemorrhagic, disseminated intravascular coagulation, ecchymosis, epistaxis, eye hemorrhage, gastric hemorrhage, gastritis hemorrhagic, gingival bleeding, hemorrhage urinary tract, hemothorax, hematemesis, hematoma, hematochezia, hematuria, hemoptysis, hemorrhoidal hemorrhage, increased tendency to bruise, injection site hematoma, injection site hemorrhage, intra-abdominal hemorrhage, lower gastrointestinal hemorrhage, Mallory-Weiss syndrome, melaena, petechiae, rectal hemorrhage, renal hemorrhage, retroperitoneal hemorrhage, small intestinal hemorrhage, splinter hemorrhages, subcutaneous hematoma, subdural hematoma, subarachnoid hemorrhage, thrombotic thrombocytopenic purpura, tumor hemorrhage, traumatic hematoma, and upper gastrointestinal hemorrhage
i. Includes decreased appetite and early satiety
j. Includes genital rash, infusion site rash, penile rash, perineal rash, rash, rash erythematous, rash macular, rash maculo-papular, rash papular, rash pruritic, and rash pustular
k. Includes palmar erythema, palmar-plantar erythrodysesthesia syndrome and plantar erythema
l. Includes hemoglobinuria, nephrotic syndrome, and proteinuria
m. Includes acute kidney injury, azotaemia, blood creatinine increased, creatinine renal clearance decreased, hypercreatininaemia, renal failure, renal impairment, oliguria, glomerular filtration rate decreased, and nephropathy toxic
n. Includes alanine aminotransferase increased, aspartate aminotransferase increased, blood bilirubin increased, drug-induced liver injury, hepatic enzyme increased, hepatic failure, hepatic function abnormal, hepatocellular injury, hepatotoxicity, hyperbilirubinemia, hypertransaminasemia, immune-mediated hepatitis, liver function test increased, liver injury, transaminases increased, and gamma-glutamyltransferase increased

Clinically relevant adverse reactions (<20%) that occurred in patients receiving LENVIMA/pembrolizumab were myocardial infarction (3%) and angina pectoris (1%).

Table 6: Laboratory Abnormalities in ≥20% (All Grades) of Patients on LENVIMA plus Pembrolizumab in CLEAR (RCC)
 | LENVIMA 20 mg in combination with Pembrolizumab 200 mg |  | Sunitinib 50 mg
Laboratory Abnormalitya | All Grades % b | Grades 3-4 % b | All Grades % b | Grade 3-4 % b
Chemistry
Hypertriglyceridemia | 80 | 15 | 71 | 15
Hypercholesterolemia | 64 | 5 | 43 | 1
Increased lipase | 61 | 34 | 59 | 28
Increased creatinine | 61 | 5 | 61 | 2
Increased amylase | 59 | 17 | 41 | 9
Increased aspartate aminotransferase (AST) | 58 | 7 | 57 | 3
Hyperglycemia | 55 | 7 | 48 | 3
Increased alanine aminotransferase (ALT) | 52 | 7 | 49 | 4
Hyperkalemia | 44 | 9 | 28 | 6
Hypoglycemia | 44 | 2 | 27 | 1
Hyponatremia | 41 | 12 | 28 | 9
Decreased albumin | 34 | 0.3 | 22 | 0
Increased alkaline phosphatase | 32 | 4 | 32 | 1
Hypocalcemia | 30 | 2 | 22 | 1
Hypophosphatemia | 29 | 7 | 50 | 8
Hypomagnesemia | 25 | 2 | 15 | 3
Increased creatine phosphokinase | 24 | 6 | 36 | 5
Hypermagnesemia | 23 | 2 | 22 | 3
Hypercalcemia | 21 | 1 | 11 | 1
Hematology
Lymphopenia | 54 | 9 | 66 | 15
Thrombocytopenia | 39 | 2 | 73 | 13
Anemia | 38 | 3 | 66 | 8
Leukopenia | 34 | 1 | 77 | 8
Neutropenia | 31 | 4 | 72 | 16
a. With at least 1 grade increase from baseline
b. Laboratory abnormality percentage is based on the number of patients who had both baseline and at least one post baseline laboratory measurement for each parameter. LENVIMA/pembrolizumab (n= 343 to 349) and sunitinib (n= 329 to 335).

Grade 3 and 4 increased ALT or AST was seen in 9% of patients. Grade ≥2 increased ALT or AST was reported in 64 (18%) patients, of whom 20 (31%) received ≥40 mg daily oral prednisone equivalent. Recurrence of Grade ≥2 increased ALT or AST was observed in 3 patients on rechallenge in patients receiving LENVIMA and 10 patients receiving both LENVIMA and pembrolizumab.

Previously Treated Renal Cell Carcinoma in Combination with Everolimus (Study 205)

The safety of LENVIMA was evaluated in Study 205, in which patients with unresectable advanced or metastatic renal cell carcinoma (RCC) were randomized (1:1:1) to LENVIMA 18 mg orally once daily with everolimus 5 mg orally once daily (n=51), LENVIMA 24 mg orally once daily (n=52), or everolimus 10 mg orally once daily (n=50) [see Clinical Studies (14.2)]. This data also includes patients on the dose escalation portion of the study who received LENVIMA with everolimus (n=11). The median treatment duration was 8.1 months for LENVIMA with everolimus. Among 62 patients who received LENVIMA with everolimus, the median age was 61 years, 71% were men, and 98% were White.

The most common adverse reactions observed in the LENVIMA with everolimus-treated group (≥30%) were, in order of decreasing frequency, diarrhea, fatigue, arthralgia/myalgia, decreased appetite, vomiting, nausea, stomatitis/oral inflammation, hypertension, peripheral edema, cough, abdominal pain, dyspnea, rash, decreased weight, hemorrhagic events, and proteinuria. The most common serious adverse reactions (≥5%) were renal failure (11%), dehydration (10%), anemia (6%), thrombocytopenia (5%), diarrhea (5%), vomiting (5%), and dyspnea (5%).

Adverse reactions led to dose reductions or interruption in 89% of patients receiving LENVIMA with everolimus. The most common adverse reactions (≥5%) resulting in dose reductions in the LENVIMA with everolimus-treated group were diarrhea (21%), fatigue (8%), thrombocytopenia (6%), vomiting (6%), nausea (5%), and proteinuria (5%).

Treatment discontinuation due to an adverse reaction occurred in 29% of patients in the LENVIMA with everolimus-treated group.

Table 7 presents the adverse reactions in >15% of patients in the LENVIMA with everolimus arm. Study 205 was not designed to demonstrate a statistically significant difference in adverse reaction rates for LENVIMA in combination with everolimus, as compared to everolimus for any specific adverse reaction listed in Table 7.

Table 7: Adverse Reactions Occurring in >15% of Patients in the LENVIMA with Everolimus Arm in Study 205 (RCC)
 | LENVIMA 18 mg with Everolimus 5 mg N=62 |  | Everolimus 10 mg N=50
Adverse Reactions | Grade 1-4 (%) | Grade 3-4 (%) | Grade 1-4 (%) | Grade 3-4 (%)
Endocrine
Hypothyroidism | 24 | 0 | 2 | 0
Gastrointestinal
Diarrhea | 81 | 19 | 34 | 2
Vomiting | 48 | 7 | 12 | 0
Nausea | 45 | 5 | 16 | 0
Stomatitis/Oral inflammationa | 44 | 2 | 50 | 4
Abdominal painb | 37 | 3 | 8 | 0
Oral painc | 23 | 2 | 4 | 0
Dyspepsia/Gastro-esophageal reflux | 21 | 0 | 12 | 0
Constipation | 16 | 0 | 18 | 0
General
Fatigued | 73 | 18 | 40 | 2
Peripheral edema | 42 | 2 | 20 | 0
Pyrexia/Increased body temperature | 21 | 2 | 10 | 2
Metabolism and Nutrition
Decreased appetite | 53 | 5 | 18 | 0
Decreased weight | 34 | 3 | 8 | 0
Musculoskeletal and Connective Tissue
Arthralgia/Myalgiae | 55 | 5 | 32 | 0
Musculoskeletal chest pain | 18 | 2 | 4 | 0
Nervous System
Headache | 19 | 2 | 10 | 2
Psychiatric
Insomnia | 16 | 2 | 2 | 0
Renal and Urinary
Proteinuria/Urine protein present | 31 | 8 | 14 | 2
Renal failure eventf | 18 | 10 | 12 | 2
Respiratory, Thoracic and Mediastinal
Cough | 37 | 0 | 30 | 0
Dyspnea/Exertional dyspnea | 35 | 5 | 28 | 8
Dysphonia | 18 | 0 | 4 | 0
Skin and Subcutaneous Tissue
Rashg | 35 | 0 | 40 | 0
Vascular
Hypertension/Increased blood pressure | 42 | 13 | 10 | 2
Hemorrhagic eventsh | 32 | 6 | 26 | 2
a Includes aphthous stomatitis, gingival inflammation, glossitis, and mouth ulceration
b Includes abdominal discomfort, gastrointestinal pain, lower abdominal pain, and upper abdominal pain
c Includes gingival pain, glossodynia, and oropharyngeal pain
d Includes asthenia, fatigue, lethargy and malaise
e Includes arthralgia, back pain, extremity pain, musculoskeletal pain, and myalgia
f Includes blood creatinine increased, blood urea increased, creatinine renal clearance decreased, nephropathy toxic, renal failure, renal failure acute, and renal impairment
g Includes erythema, erythematous rash, genital rash, macular rash, maculo-papular rash, papular rash, pruritic rash, pustular rash, and septic rash
h Includes hemorrhagic diarrhea, epistaxis, gastric hemorrhage, hemarthrosis, hematoma, hematuria, hemoptysis, lip hemorrhage, renal hematoma, and scrotal hematocele

In Table 8, Grade 3-4 laboratory abnormalities occurring in ≥3% of patients in the LENVIMA with everolimus arm are presented.

Table 8: Grade 3-4 Laboratory Abnormalities Occurring in ≥3% of Patients in the LENVIMA with Everolimus Arma, b in Study 205 (RCC)
Laboratory Abnormality | LENVIMA 18 mg with Everolimus 5 mg | Everolimus 10 mg
 | Grades 3-4 (%) | Grades 3-4 (%)
Chemistry
Hypertriglyceridemia | 18 | 18
Increased lipase | 13 | 12
Hypercholesterolemia | 11 | 0
Hyponatremia | 11 | 6
Hypophosphatemia | 11 | 6
Hyperkalemia | 6 | 2
Hypocalcemia | 6 | 2
Hypokalemia | 6 | 2
Increased aspartate aminotransferase (AST) | 3 | 0
Increased alanine aminotransferase (ALT) | 3 | 2
Increased alkaline phosphatase | 3 | 0
Hyperglycemia | 3 | 16
Increased creatine kinase | 3 | 4
Hematology
Lymphopenia | 10 | 20
Anemia | 8 | 16
Thrombocytopenia | 5 | 0
a. With at least 1 grade increase from baseline
b. Laboratory Abnormality percentage is based on the number of patients who had both baseline and at least one post baseline laboratory measurement for each parameter. LENVIMA with Everolimus (n = 62), Everolimus (n = 50).

Hepatocellular Carcinoma

The safety of LENVIMA was evaluated in REFLECT, which randomized (1:1) patients with unresectable hepatocellular carcinoma (HCC) to LENVIMA (n=476) or sorafenib (n=475) [see Clinical Studies (14.3)]. The dose of LENVIMA was 12 mg orally once daily for patients with a baseline body weight of ≥60 kg and 8 mg orally once daily for patients with a baseline body weight of <60 kg. The dose of sorafenib was 400 mg orally twice daily. Duration of treatment was ≥6 months in 49% and 32% of patients in the LENVIMA and sorafenib groups, respectively. Among the 476 patients who received LENVIMA in REFLECT, the median age was 63 years, 85% were men, 28% were White and 70% were Asian.

The most common adverse reactions observed in the LENVIMA-treated patients (≥20%) were, in order of decreasing frequency, hypertension, fatigue, diarrhea, decreased appetite, arthralgia/myalgia, decreased weight, abdominal pain, palmar-plantar erythrodysesthesia syndrome, proteinuria, dysphonia, hemorrhagic events, hypothyroidism, and nausea.

The most common serious adverse reactions (≥2%) in LENVIMA-treated patients were hepatic encephalopathy (5%), hepatic failure (3%), ascites (3%), and decreased appetite (2%).

Adverse reactions led to dose reduction or interruption in 62% of patients receiving LENVIMA. The most common adverse reactions (≥5%) resulting in dose reduction or interruption of LENVIMA were fatigue (9%), decreased appetite (8%), diarrhea (8%), proteinuria (7%), hypertension (6%), and palmar-plantar erythrodysesthesia syndrome (5%).

Treatment discontinuation due to adverse reactions occurred in 20% of patients in the LENVIMA-treated group. The most common adverse reactions (≥1%) resulting in discontinuation of LENVIMA were fatigue (1%), hepatic encephalopathy (2%), hyperbilirubinemia (1%), and hepatic failure (1%).

Table 9 summarizes the adverse reactions that occurred in ≥10% of patients receiving LENVIMA in REFLECT. REFLECT was not designed to demonstrate a statistically significant reduction in adverse reaction rates for LENVIMA, as compared to sorafenib, for any specified adverse reaction listed in Table 9.

Table 9: Adverse Reactions Occurring in ≥10% of Patients in the LENVIMA Arm in REFLECT (HCC)
Adverse Reaction | LENVIMA 8 mg/12 mg N=476 |  | Sorafenib 800 mg N=475
 | Grade 1-4 (%) | Grade 3-4 (%) | Grade 1-4 (%) | Grade 3-4 (%)
Endocrine
Hypothyroidisma | 21 | 0 | 3 | 0
Gastrointestinal
Diarrhea | 39 | 4 | 46 | 4
Abdominal painb | 30 | 3 | 28 | 4
Nausea | 20 | 1 | 14 | 1
Vomiting | 16 | 1 | 8 | 1
Constipation | 16 | 1 | 11 | 0
Ascitesc | 15 | 4 | 11 | 3
Stomatitisd | 11 | 0.4 | 14 | 1
General
Fatiguee | 44 | 7 | 36 | 6
Pyrexiaf | 15 | 0 | 14 | 0.2
Peripheral edema | 14 | 1 | 7 | 0.2
Metabolism and Nutrition
Decreased appetite | 34 | 5 | 27 | 1
Decreased weight | 31 | 8 | 22 | 3
Musculoskeletal and Connective Tissue
Arthralgia/Myalgiag | 31 | 1 | 20 | 2
Nervous System
Headache | 10 | 1 | 8 | 0
Renal and Urinary
Proteinuriah | 26 | 6 | 12 | 2
Respiratory, Thoracic and Mediastinal
Dysphonia | 24 | 0.2 | 12 | 0
Skin and Subcutaneous Tissue
Palmar-plantar erythrodysesthesia syndrome | 27 | 3 | 52 | 11
Rashi | 14 | 0 | 24 | 2
Vascular
Hypertensionj | 45 | 24 | 31 | 15
Hemorrhagic eventsk | 23 | 4 | 15 | 4
a. Includes hypothyroidism, blood thyroid stimulating hormone increased.
b. Includes abdominal discomfort, abdominal pain, abdominal tenderness, epigastric discomfort, gastrointestinal pain, lower abdominal pain, and upper abdominal pain
c. Includes ascites and malignant ascites
d. Includes aphthous ulcer, gingival erosion, gingival ulceration, glossitis, mouth ulceration, oral mucosal blistering, and stomatitis
e. Includes asthenia, fatigue, lethargy and malaise
f. Includes increased body temperature, pyrexia
g. Includes arthralgia, back pain, extremity pain, musculoskeletal chest pain, musculoskeletal discomfort, musculoskeletal pain, and myalgia
h. Includes proteinuria, increased urine protein, protein urine present
i. Includes erythema, erythematous rash, exfoliative rash, genital rash, macular rash, maculo-papular rash, papular rash, pruritic rash, pustular rash and rash
j. Includes increased diastolic blood pressure, increased blood pressure, hypertension and orthostatic hypertension
k. Includes all hemorrhage terms. Hemorrhage terms that occurred in 5 or more subjects in either treatment group include: epistaxis, hematuria, gingival bleeding, hemoptysis, esophageal varices hemorrhage, hemorrhoidal hemorrhage, mouth hemorrhage, rectal hemorrhage and upper gastrointestinal hemorrhage

In Table 10, Grade 3-4 laboratory abnormalities occurring in ≥2% of patients in the LENVIMA arm in REFLECT (HCC) are presented.

Table 10: Grade 3-4 Laboratory Abnormalities Occurring in ≥2% of Patients in the LENVIMA Arma,b in REFLECT (HCC)
Laboratory Abnormality | LENVIMA (%) | Sorafenib (%)
Chemistry
Increased GGT | 17 | 20
Hyponatremia | 15 | 9
Hyperbilirubinemia | 13 | 10
Increased aspartate aminotransferase (AST) | 12 | 18
Increased alanine aminotransferase (ALT) | 8 | 9
Increased alkaline phosphatase | 7 | 5
Increased lipase | 6 | 17
Hypokalemia | 3 | 4
Hyperkalemia | 3 | 2
Decreased albumin | 3 | 1
Increased creatinine | 2 | 2
Hematology
Thrombocytopenia | 10 | 8
Lymphopenia | 8 | 9
Neutropenia | 7 | 3
Anemia | 4 | 5
a. With at least 1 grade increase from baseline
b. Laboratory Abnormality percentage is based on the number of patients who had both baseline and at least one post baseline laboratory measurement for each parameter. LENVIMA (n=278 to 470) and sorafenib (n=260 to 473)

Endometrial Carcinoma

The safety of LENVIMA in combination with pembrolizumab was investigated in Study 309, a multicenter, open-label, randomized (1:1), active-controlled trial in patients with advanced endometrial carcinoma previously treated with at least one prior platinum-based chemotherapy regimen in any setting, including in the neoadjuvant and adjuvant settings [see Clinical Studies (14.4)]. Patients with endometrial carcinoma that are pMMR or not MSI-H received LENVIMA 20 mg orally once daily with pembrolizumab 200 mg intravenously every 3 weeks (n=342); or received doxorubicin or paclitaxel (n= 325).

For patients with pMMR or not MSI-H status, the median duration of study treatment was 7.2 months (range 1 day to 26.8 months) and the median duration of exposure to LENVIMA was 6.7 months (range: 1 day to 26.8 months).

Fatal adverse reactions among these patients occurred in 4.7% of those treated with LENVIMA and pembrolizumab, including 2 cases of pneumonia, and 1 case of the following: acute kidney injury, acute myocardial infarction, colitis, decreased appetite, intestinal perforation, lower gastrointestinal hemorrhage, malignant gastrointestinal obstruction, multiple organ dysfunction syndrome, myelodysplastic syndrome, pulmonary embolism, and right ventricular dysfunction.

Serious adverse reactions occurred in 50% of these patients receiving LENVIMA and pembrolizumab. Serious adverse reactions with frequency ≥3% were hypertension (4.4%), and urinary tract infection (3.2%).

Discontinuation of LENVIMA due to an adverse reaction occurred in 26% of these patients. The most common (≥1 %) adverse reactions leading to discontinuation of LENVIMA were hypertension (2%), asthenia (1.8%), diarrhea (1.2%), decreased appetite (1.2%), proteinuria (1.2%), and vomiting (1.2%).

Dose reductions of LENVIMA due to adverse reactions occurred in 67% of patients. The most common (≥5%) adverse reactions resulting in dose reduction of LENVIMA were hypertension (18%), diarrhea (11%), palmar-plantar erythrodysesthesia syndrome (9%), proteinuria (7%), fatigue (7%), decreased appetite (6%), asthenia (5%), and weight decreased (5%).

Dose interruptions of LENVIMA due to an adverse reaction occurred in 58% of these patients. The most common (≥2%) adverse reactions leading to interruption of LENVIMA were hypertension (11%), diarrhea (11%), proteinuria (6%), decreased appetite (5%), vomiting (5%), increased alanine aminotransferase (3.5%), fatigue (3.5%), nausea (3.5%), abdominal pain (2.9%), weight decreased (2.6%), urinary tract infection (2.6%), increased aspartate aminotransferase (2.3%), asthenia (2.3%), and palmar-plantar erythrodysesthesia (2%).

Tables 11 and 12 summarize adverse reactions and laboratory abnormalities, respectively, in patients receiving LENVIMA in Study 309.

Table 11: Adverse Reactions in ≥20% of Patients Receiving LENVIMA plus Pembrolizumab in Study 309 (EC)
 | Endometrial Carcinoma (pMMR or not MSI-H)
 | LENVIMA 20 mg in combination with Pembrolizumab 200 mg N=342 |  | Doxorubicin or Paclitaxel N=325
Adverse Reaction | All Gradesa (%) | Grades 3-4 (%) | All Gradesa (%) | Grades 3-4 (%)
Endocrine
Hypothyroidismb | 67 | 0.9 | 0.9 | 0
Vascular
Hypertensionc | 67 | 39 | 6 | 2.5
Hemorrhagic eventsd | 25 | 2.6 | 15 | 0.9
General
Fatiguee | 58 | 11 | 54 | 6
Gastrointestinal
Diarrheaf | 55 | 8 | 20 | 2.8
Nausea | 49 | 2.9 | 47 | 1.5
Vomiting | 37 | 2.3 | 21 | 2.2
Stomatitisg | 35 | 2.6 | 26 | 1.2
Abdominal painh | 34 | 2.6 | 21 | 1.2
Constipation | 27 | 0 | 25 | 0.6
Musculoskeletal and Connective Tissue
Musculoskeletal disordersi | 53 | 5 | 27 | 0.6
Metabolism
Decreased appetitej | 44 | 7 | 21 | 0
Investigations
Decreased weight | 34 | 10 | 6 | 0.3
Renal and Urinary
Proteinuriak | 29 | 6 | 3.4 | 0.3
Infections
Urinary tract infectionl | 31 | 5 | 13 | 1.2
Nervous System
Headache | 26 | 0.6 | 9 | 0.3
Respiratory, Thoracic and Mediastinal
Dysphonia | 22 | 0 | 0.6 | 0
Skin and Subcutaneous Tissue
Palmar-plantar erythrodysesthesiam | 23 | 2.9 | 0.9 | 0
Rashn | 20 | 2.3 | 4.9 | 0
a. Graded per NCI CTCAE v4.03
b. Includes hypothyroidism, blood thyroid stimulating hormone increased, thyroiditis, primary hypothyroidism, and secondary hypothyroidism
c. Includes hypertension, blood pressure increased, hypertensive crisis, secondary hypertension, blood pressure abnormal, hypertensive encephalopathy, and blood pressure fluctuation
d. Includes epistaxis, vaginal hemorrhage, hematuria, gingival bleeding, metrorrhagia, rectal hemorrhage, contusion, hematochezia, cerebral hemorrhage, conjunctival hemorrhage, gastrointestinal hemorrhage, hemoptysis, hemorrhage urinary tract, lower gastrointestinal hemorrhage, mouth hemorrhage, petechiae, uterine hemorrhage, anal hemorrhage, blood blister, eye hemorrhage, hematoma, hemorrhage intracranial, hemorrhagic stroke, injection site hemorrhage, melena, purpura, stoma site hemorrhage, upper gastrointestinal hemorrhage, wound hemorrhage, blood urine present, coital bleeding, ecchymosis, hematemesis, hemorrhage subcutaneous, hepatic hematoma, injection site bruising, intestinal hemorrhage, laryngeal hemorrhage, pulmonary hemorrhage, subdural hematoma, umbilical hemorrhage, and vessel puncture site bruise
e. Includes fatigue, asthenia, malaise, and lethargy
f. Includes diarrhea and gastroenteritis
g. Includes stomatitis, mucosal inflammation, oropharyngeal pain, aphthous ulcer, mouth ulceration, cheilitis, oral mucosal erythema, and tongue ulceration
h. Includes abdominal pain, abdominal pain upper, abdominal pain lower, abdominal discomfort, gastrointestinal pain, abdominal tenderness, and epigastric discomfort
i. Includes arthralgia, myalgia, back pain, pain in extremity, bone pain, neck pain, musculoskeletal pain, arthritis, musculoskeletal chest pain, musculoskeletal stiffness, non-cardiac chest pain, pain in jaw
j. Includes decreased appetite and early satiety
k. Includes proteinuria, protein urine present, hemoglobinuria
l. Includes urinary tract infection, cystitis, and pyelonephritis
m. Includes palmar-plantar erythrodysesthesia syndrome, palmar erythema, plantar erythema, and skin reaction
n. Includes rash, rash maculo-papular, rash pruritic, rash erythematous, rash macular, rash pustular, rash papular, rash vesicular, and application site rash

Table 12: Laboratory Abnormalities Worsened from Baselinea Occurring in ≥20% (All Grades) or ≥3% (Grades 3-4) of Patients Receiving LENVIMA plus Pembrolizumab in Study 309 (EC)
 | Endometrial Carcinoma (pMMR or not MSI-H)
 | LENVIMA 20 mg in combination with Pembrolizumab 200 mg N=342 |  | Doxorubicin or Paclitaxel N=325
Laboratory Testb | All Gradesc (%) | Grades 3-4 (%) | All Gradesc (%) | Grades 3-4 (%)
Chemistry
Hypertriglyceridemia | 70 | 6 | 45 | 1.7
Hypoalbuminemia | 60 | 2.7 | 42 | 1.6
Increased aspartate aminotransferase | 58 | 9 | 23 | 1.6
Hyperglycemia | 58 | 8 | 45 | 4.4
Hypomagnesemia | 46 | 0 | 27 | 1.3
Increased alanine aminotransferase | 55 | 9 | 21 | 1.2
Hypercholesteremia | 53 | 3.2 | 23 | 0.7
Hyponatremia | 46 | 15 | 28 | 7
Increased alkaline phosphatase | 43 | 4.7 | 18 | 0.9
Hypocalcemia | 40 | 4.7 | 21 | 1.9
Increased lipase | 36 | 14 | 13 | 3.9
Increased creatinine | 35 | 4.7 | 18 | 1.9
Hypokalemia | 34 | 10 | 24 | 5
Hypophosphatemia | 26 | 8 | 17 | 3.2
Increased amylase | 25 | 7 | 8 | 1
Hyperkalemia | 23 | 2.4 | 12 | 1.2
Increased creatine kinase | 19 | 3.7 | 7 | 0
Increased bilirubin | 18 | 3.6 | 6 | 1.6
Hematology
Lymphopenia | 51 | 18 | 66 | 23
Thrombocytopenia | 50 | 8 | 30 | 4.7
Anemia | 49 | 8 | 84 | 14
Leukopenia | 43 | 3.5 | 83 | 43
Neutropenia | 34 | 8 | 80 | 60
a. With at least 1 grade increase from baseline
b. Laboratory abnormality percentage is based on the number of patients who had both baseline and at least one post-baseline laboratory measurement for each parameter: LENVIMA/pembrolizumab (range: 263 to 340 patients) and doxorubicin or paclitaxel (range: 240 to 322 patients).
c. Graded per NCI CTCAE v4.03

6.2 Postmarketing Experience

The following adverse reactions have been identified during post-approval use of LENVIMA. Because these reactions are reported voluntarily from a population of uncertain size, it is not always possible to reliably estimate their frequency or establish a causal relationship to drug exposure.

Gastrointestinal: pancreatitis, increased amylase

General: impaired wound healing

Hepatobiliary: cholecystitis

Renal and Urinary: nephrotic syndrome

Vascular: arterial (including aortic) aneurysms, dissections, and rupture

7 DRUG INTERACTIONS

7.1 Drugs That Prolong the QT Interval

LENVIMA has been reported to prolong the QT/QTc interval. Avoid coadministration of LENVIMA with medicinal products with a known potential to prolong the QT/QTc interval [see Warnings and Precautions (5.9)].

8 USE IN SPECIFIC POPULATIONS

8.1 Pregnancy

Risk Summary

Based on findings from animal studies and its mechanism of action, LENVIMA can cause fetal harm when administered to a pregnant woman [see Clinical Pharmacology (12.1)]. In animal reproduction studies, oral administration of lenvatinib during organogenesis at doses below the recommended human doses resulted in embryotoxicity, fetotoxicity, and teratogenicity in rats and rabbits (see Data). There are no available human data informing the drug-associated risk. Advise pregnant women of the potential risk to a fetus.

In the U.S. general population, the estimated background risk of major birth defects and miscarriage in clinically recognized pregnancies is 2% to 4% and 15% to 20%, respectively.

Data

Animal Data

In an embryofetal development study, daily oral administration of lenvatinib mesylate at doses ≥0.3 mg/kg [approximately 0.14 times the recommended clinical dose of 24 mg based on body surface area (BSA)] to pregnant rats during organogenesis resulted in dose-related decreases in mean fetal body weight, delayed fetal ossifications, and dose-related increases in fetal external (parietal edema and tail abnormalities), visceral, and skeletal anomalies. Greater than 80% post-implantation loss was observed at 1.0 mg/kg/day (approximately 0.5 times the recommended clinical dose of 24 mg based on BSA).

Daily oral administration of lenvatinib mesylate to pregnant rabbits during organogenesis resulted in fetal external (short tail), visceral (retroesophageal subclavian artery), and skeletal anomalies at doses greater than or equal to 0.03 mg/kg (approximately 0.03 times the recommended clinical dose of 24 mg based on BSA). At the 0.03 mg/kg dose, increased post-implantation loss, including 1 fetal death, was also observed. Lenvatinib was abortifacient in rabbits, resulting in late abortions in approximately one-third of the rabbits treated at a dose level of 0.5 mg/kg/day (approximately 0.5 times the recommended clinical dose of 24 mg based on BSA).

8.2 Lactation

Risk Summary

It is not known whether LENVIMA is present in human milk; however, lenvatinib and its metabolites are excreted in rat milk at concentrations higher than those in maternal plasma (see Data). Because of the potential for serious adverse reactions in breastfed children, advise women to discontinue breastfeeding during treatment with LENVIMA and for 1 week after the last dose.

Data

Animal Data

Following administration of radiolabeled lenvatinib to lactating Sprague Dawley rats, lenvatinib-related radioactivity was approximately 2 times higher [based on area under the curve (AUC)] in milk compared to maternal plasma.

8.3 Females and Males of Reproductive Potential

Based on animal data and its mechanism of action, LENVIMA can cause fetal harm when administered to a pregnant woman [see Use in Specific Populations (8.1)].

Pregnancy Testing

Verify the pregnancy status of females of reproductive potential prior to initiating LENVIMA [see Use in Specific Populations (8.1)].

Contraception

Females

Advise females of reproductive potential of the potential risk to a fetus and to use effective contraception during treatment with LENVIMA and for 30 days after the last dose.

Infertility

LENVIMA may impair fertility in males and females of reproductive potential [see Nonclinical Toxicology (13.1)].

8.4 Pediatric Use

The safety and effectiveness of LENVIMA in pediatric patients have not been established.

The safety and efficacy of LENVIMA alone and in combination were investigated but not established in four open label studies (NCT02432274, NCT04154189, NCT04447755, NCT03245151) in 232 patients aged 2 to <17 years with relapsed or refractory solid tumors, including osteosarcoma, Ewing sarcoma, rhabdomyosarcoma, and high-grade glioma. Hypothyroidism and pneumothorax were observed at a higher rate in pediatric patients compared to that of adult patients. The pharmacokinetics (PK) of lenvatinib in pediatric patients were within range of values previously observed in adults at the approved recommended dose of 24 mg.

Juvenile Animal Data

Daily oral administration of lenvatinib mesylate to juvenile rats for 8 weeks starting on postnatal day 21 (approximately equal to a human pediatric age of 2 years) resulted in growth retardation (decreased body weight gain, decreased food consumption, and decreases in the width and/or length of the femur and tibia) and secondary delays in physical development and reproductive organ immaturity at doses greater than or equal to 2 mg/kg (approximately 1.2 to 5 times the human exposure based on AUC at the recommended clinical dose of 24 mg). Decreased length of the femur and tibia persisted following 4 weeks of recovery. In general, the toxicologic profile of lenvatinib was similar between juvenile and adult rats, though toxicities including broken teeth at all dose levels and mortality at the 10 mg/kg/day dose level (attributed to primary duodenal lesions) occurred at earlier treatment time-points in juvenile rats.

8.5 Geriatric Use

Of the 261 patients with differentiated thyroid cancer (DTC) who received LENVIMA in SELECT, 45% were ≥65 years of age and 11% were ≥75 years of age. No overall differences in safety or effectiveness were observed between these subjects and younger subjects.

Of the 352 patients with renal cell carcinoma (RCC) who received LENVIMA with pembrolizumab in CLEAR, 45% were ≥65 years of age and 13% were ≥75 years of age. No overall differences in safety or effectiveness were observed between these elderly patients and younger patients.

Of the 62 patients with RCC who received LENVIMA with everolimus in Study 205, 36% were ≥65 years of age. Conclusions are limited due to the small sample size, but there appeared to be no overall differences in safety or effectiveness between these subjects and younger subjects.

Of the 476 patients with hepatocellular carcinoma (HCC) who received LENVIMA in REFLECT, 44% were ≥65 years of age and 12% were ≥75 years of age. No overall differences in safety or effectiveness were observed between patients ≥65 and younger subjects. Patients ≥75 years of age showed reduced tolerability to LENVIMA.

Of 406 adult patients with endometrial carcinoma (EC) who were treated with LENVIMA in combination with pembrolizumab in Study 309, 201 (50%) were 65 years and over. No overall differences in safety or effectiveness were observed between elderly patients and younger patients.

8.6 Renal Impairment

No dose adjustment is recommended for patients with mild (CLcr 60-89 mL/min) or moderate (CLcr 30-59 mL/min) renal impairment. Lenvatinib concentrations may increase in patients with DTC, RCC, or endometrial carcinoma and severe (CLcr 15-29 mL/min) renal impairment. Reduce the dose of LENVIMA for patients with RCC, DTC, or endometrial carcinoma and severe renal impairment [see Dosage and Administration (2.7)]. There is no recommended dose of LENVIMA for patients with HCC and severe renal impairment. LENVIMA has not been studied in patients with end stage renal disease [see Warnings and Precautions (5.5), Clinical Pharmacology (12.3)].

8.7 Hepatic Impairment

No dose adjustment is recommended for patients with HCC and mild hepatic impairment (Child-Pugh A). There is no recommended dose for patients with HCC with moderate or severe hepatic impairment.

No dose adjustment is recommended for patients with DTC, RCC, or endometrial carcinoma and mild or moderate hepatic impairment (Child-Pugh A or B). Lenvatinib concentrations may increase in patients with DTC, RCC, or endometrial carcinoma and severe hepatic impairment (Child-Pugh C). Reduce the dose of lenvatinib for patients with DTC, RCC, or endometrial carcinoma and severe hepatic impairment [see Dosage and Administration (2.7), Clinical Pharmacology (12.3)].

10 OVERDOSAGE

Due to the high plasma protein binding, lenvatinib is not expected to be dialyzable [see Clinical Pharmacology (12.3)]. Death due to multiorgan dysfunction occurred in a patient who received a single dose of LENVIMA 120 mg orally.

11 DESCRIPTION

LENVIMA, a kinase inhibitor, is the mesylate salt of lenvatinib. Its chemical name is 4-[3-chloro-4-(N’-cyclopropylureido)phenoxy]-7-methoxyquinoline-6-carboxamide methanesulfonate. The molecular formula is C21H19ClN4O4 • CH4O3S, and the molecular weight of the mesylate salt is 522.96. The chemical structure of lenvatinib mesylate is:

Lenvatinib mesylate is a white to pale reddish yellow powder. It is slightly soluble in water and practically insoluble in ethanol (dehydrated). The dissociation constant (pKa value) of lenvatinib mesylate is 5.05 at 25°C. The partition coefficient (log P value) is 3.3.

LENVIMA capsules for oral administration contain 4 mg or 10 mg of lenvatinib, equivalent to 4.90 mg or 12.25 mg of lenvatinib mesylate, respectively. The inactive ingredients are: calcium carbonate, hydroxypropyl cellulose, low-substituted hydroxypropyl cellulose, mannitol, microcrystalline cellulose, and talc.

In addition, the capsule shell contains ferric oxide red, ferric oxide yellow, hypromellose, and titanium dioxide. The printing ink contains black iron oxide, potassium hydroxide, propylene glycol, and shellac.

12 CLINICAL PHARMACOLOGY

12.1 Mechanism of Action

Lenvatinib is a kinase inhibitor that inhibits the kinase activities of vascular endothelial growth factor (VEGF) receptors VEGFR1 (FLT1), VEGFR2 (KDR), and VEGFR3 (FLT4). Lenvatinib inhibits other kinases that have been implicated in pathogenic angiogenesis, tumor growth, and cancer progression in addition to their normal cellular functions, including fibroblast growth factor (FGF) receptors FGFR1, 2, 3, and 4; platelet derived growth factor receptor alpha (PDGFRA), KIT, and RET. Lenvatinib also exhibited antiproliferative activity in hepatocellular carcinoma cell lines dependent on activated FGFR signaling with a concurrent inhibition of FGF-receptor substrate 2 alpha (FRS2) phosphorylation.

In syngeneic mouse tumor models, lenvatinib decreased tumor-associated macrophages, increased activated cytotoxic T cells, and demonstrated greater antitumor activity in combination with an anti-PD-1 monoclonal antibody compared to either treatment alone.

The combination of lenvatinib and everolimus showed increased antiangiogenic and antitumor activity as demonstrated by decreases in human endothelial cell proliferation, tube formation, and VEGF signaling in vitro, and by decreases in tumor volume in mouse xenograft models of human renal cell cancer that were greater than those with either drug alone.

12.2 Pharmacodynamics

Exposure-Response Relationships

In a multicenter randomized (1:1) double blind trial of 152 patients with radioactive iodine (RAI)-refractory DTC, a dose-response relationship for overall response rate (ORR) was observed over the dose range of 18 mg (0.75 times the recommended dose of 24 mg) and 24 mg. A higher ORR was observed at the recommended lenvatinib dose.

No dose-response relationships for adverse reactions, serious adverse reactions, adverse reactions leading to study drug discontinuation, and adverse reactions leading to study drug interruption were observed over the same dose range.

12.3 Pharmacokinetics

In patients with solid tumors administered single and multiple doses of LENVIMA once daily, the maximum lenvatinib plasma concentration (Cmax) and the area under the concentration-time curve (AUC) increased proportionally over the dose range of 3.2 mg (0.1 times the recommended clinical dose of 24 mg) to 32 mg (1.33 times the recommended clinical dose of 24 mg) with a median accumulation index of 0.96 (20 mg) to 1.54 (6.4 mg).

Geometric mean Cmax and AUC values at steady state for RCC, DTC and HCC are summarized in the Table 13.

Table 13: Lenvatinib Cmax and AUC in Patients with Solid Tumorsa
Tumor Type | Dose | Parameter | N | Geometric Mean | %CV
RCC | 18 mg | Cmax (ng/mL) | 350 | 267 | 36.7
 |  | AUC (ng∙h/mL) | 350 | 3148 | 42.5
 | 20 mg | Cmax (ng/mL) | 346 | 275 | 32.6
 |  | AUC (ng∙h/mL) | 346 | 3135 | 41.3
DTC | 24 mg | Cmax (ng/mL) | 251 | 323 | 33.3
 |  | AUC (ng∙h/mL) | 251 | 3483 | 34.7
HCC (body weight < 60 kg) | 8 mg | Cmax (ng/mL) | 150 | 154 | 25.4
 |  | AUC (ng∙h/mL) | 150 | 1835 | 34.0
HCC (body weight ≥ 60 kg) | 12 mg | Cmax (ng/mL) | 318 | 172 | 23.1
 |  | AUC (ng∙h/mL) | 318 | 2013 | 29.3

a Model-predicted steady-state pharmacokinetic parameters are presented.

Absorption

The time to peak plasma concentration (Tmax) typically occurred from 1 to 4 hours post-dose.

Food Effect

Administration with a high fat meal (approximately 900 calories of which approximately 55% were from fat, 15% from protein, and 30% from carbohydrates) did not affect the extent of absorption, but decreased the rate of absorption and delayed the median Tmax from 2 hours to 4 hours.

Distribution

Model-predicted geometric mean steady state volume of distribution is 97 L (%CV, 30.2%). Protein binding of lenvatinib is 97% to 99%, which is independent of concentration, and is not impacted by hepatic or renal function. The blood-to-plasma concentration ratio ranged from 0.59 to 0.61 at concentrations of 0.1 to 10 μg/mL in vitro.

Elimination

The terminal elimination half-life of lenvatinib was approximately 28 hours.

Metabolism

The main metabolic pathways for lenvatinib in humans were identified as enzymatic (CYP3A and aldehyde oxidase) and non-enzymatic processes.

Excretion

Ten days after a single administration of radiolabeled lenvatinib, approximately 64% and 25% of the radiolabel were eliminated in the feces and urine, respectively.

Specific Populations

Age (18 to 92 years), sex, race/ethnicity (White, Black and Asian), tumor types (DTC, RCC, HCC and other tumor types) and renal impairment (creatinine clearance: 15-89 mL/min) did not have a significant effect on apparent oral clearance (CL/F). Subjects with end stage renal disease were not studied.

Patients with Hepatic Impairment

The pharmacokinetics of lenvatinib following a single 10 mg dose were evaluated in subjects with mild (Child-Pugh A) or moderate (Child-Pugh B) hepatic impairment. The pharmacokinetics of a single 5 mg dose were evaluated in subjects with severe (Child-Pugh C) hepatic impairment. Compared to subjects with normal hepatic function, the dose-adjusted AUC0-inf of lenvatinib for subjects with mild, moderate, and severe hepatic impairment were 119%, 107%, and 180%, respectively.

Apparent oral clearance of lenvatinib in patients with HCC and mild hepatic impairment was similar to patients with HCC and moderate hepatic impairment.

Body Weight

Lenvatinib exposures in patients with HCC in REFLECT were comparable between those weighing <60 kg who received a starting dose of 8 mg and those ≥60 kg who received a starting dose of 12 mg.

Drug Interaction Studies

Effect of Other Drugs on Lenvatinib

CYP3A, P-gp, and BCRP Inhibitors: Ketoconazole (400 mg daily for 18 days) increased lenvatinib (administered as a single 5 mg dose on Day 5) AUC by 15% and Cmax by 19%.

P-gp Inhibitor: Rifampicin (600 mg as a single dose) increased lenvatinib (24 mg as a single dose) AUC by 31% and Cmax by 33%.

CYP3A and P-gp Inducers: Rifampicin (600 mg daily for 21 days) decreased lenvatinib (24 mg as a single dose on Day 15) AUC by 18%. The Cmax was unchanged.

Population pharmacokinetic analysis demonstrated that neither everolimus nor pembrolizumab meaningfully affect the pharmacokinetics of lenvatinib.

In Vitro Studies with Transporters: Lenvatinib is a substrate of P-gp and BCRP but not a substrate for organic anion transporter (OAT) 1, OAT3, organic anion transporting polypeptide (OATP) 1B1, OATP1B3, organic cation transporter (OCT) 1, OCT2, multidrug and toxin extrusion (MATE) 1, MATE2-K, or the bile salt export pump (BSEP).

Effect of Lenvatinib on Other Drugs

CYP2C8 Substrate: There is no projected significant drug-drug interaction risk between lenvatinib and repaglinide.

CYP3A4 Substrate: Co-administration of lenvatinib with midazolam had no effect on the pharmacokinetics of midazolam.

Population pharmacokinetic analysis demonstrated that lenvatinib does not meaningfully affect the pharmacokinetics of either everolimus or pembrolizumab.

In Vitro Studies with Substrates of CYP or UDP-glucuronosyltransferase (UGT): Lenvatinib inhibits CYP2C8, CYP1A2, CYP2B6, CYP2C9, CYP2C19, CYP2D6, and CYP3A. Lenvatinib does not inhibit CYP2A6 and CYP2E1. Lenvatinib induces CYP3A, but it does not induce CYP1A1, CYP1A2, CYP2B6, and CYP2C9.

Lenvatinib inhibits UGT1A1, UGT1A4, and UGT1A9 in vitro, but likely only inhibits UGT1A1 in vivo in the gastrointestinal tract based on the expression of the enzyme in tissues. Lenvatinib does not inhibit UGT1A6, UGT2B7 or aldehyde oxidase. Lenvatinib does not induce UGT1A1, UGT1A4, UGT1A6, UGT1A9, or UGT2B7.

In Vitro Studies with Substrates of Transporters:

Lenvatinib does not have the potential to inhibit MATE1, MATE2-K, OCT1, OCT2, OAT1, OAT3, BSEP, OATP1B1, or OATP1B3 in vivo.

13 NONCLINICAL TOXICOLOGY

13.1 Carcinogenesis, Mutagenesis, Impairment of Fertility

Carcinogenicity studies have not been conducted with lenvatinib. Lenvatinib mesylate was not mutagenic in the in vitro bacterial reverse mutation (Ames) assay. Lenvatinib was not clastogenic in the in vitro mouse lymphoma thymidine kinase assay or the in vivo rat micronucleus assay.

No specific studies with lenvatinib have been conducted in animals to evaluate the effect on fertility; however, results from general toxicology studies in rats, monkeys, and dogs suggest there is a potential for lenvatinib to impair fertility. Male dogs exhibited testicular hypocellularity of the seminiferous epithelium and desquamated seminiferous epithelial cells in the epididymides at lenvatinib exposures approximately 0.02 to 0.09 times the AUC at the recommended clinical dose of 24 mg once daily. Follicular atresia of the ovaries was observed in monkeys and rats at exposures 0.2 to 0.8 times and 10 to 44 times the AUC at the recommended clinical dose of 24 mg once daily, respectively. In addition, in monkeys, a decreased incidence of menstruation was reported at lenvatinib exposures lower than those observed in humans at the recommended clinical dose of 24 mg once daily.

14 CLINICAL STUDIES

14.1 Differentiated Thyroid Cancer

A multicenter, randomized (2:1), double-blind, placebo-controlled study (SELECT; NCT01321554) was conducted in 392 patients with locally recurrent or metastatic radioactive iodine-refractory differentiated thyroid cancer and radiographic evidence of disease progression within 12 months prior to randomization, confirmed by independent radiologic review. Radioactive iodine (RAI)-refractory was defined as 1 or more measurable lesions with no iodine uptake on RAI scan, iodine uptake with progression within 12 months of RAI therapy, or having received cumulative RAI activity >600 mCi (22 GBq) with the last dose administered at least 6 months prior to study entry. Patients were randomized to receive LENVIMA 24 mg once daily (n=261) or placebo (n=131) until disease progression. Randomization was stratified by geographic region, prior VEGF/VEGFR-targeted therapy, and age. The major efficacy outcome measure was progression-free survival (PFS) as determined by blinded independent radiologic review using Response Evaluation Criteria in Solid Tumors (RECIST) 1.1. Independent review confirmation of disease progression was required prior to discontinuing patients from the randomization phase of the study. Other efficacy outcome measures included objective response rate (ORR) and overall survival (OS). Patients in the placebo arm could receive LENVIMA following independent review confirmation of disease progression.

Of the 392 patients randomized, 51% were male, the median age was 63 years, 40% were 65 years or older, 79% were White, 54% had an Eastern Cooperative Oncology Group (ECOG) performance status (PS) of 0, and 24% had received 1 prior VEGF/VEGFR-targeted therapy. Metastases were present in 99% of the patients: lungs in 89%, lymph nodes in 52%, bone in 39%, liver in 18%, and brain in 4%. The histological diagnoses were papillary thyroid cancer (66%) and follicular thyroid cancer (34%); of those with follicular histology, 44% had Hürthle cell and 11% had clear cell subtypes. In the LENVIMA arm, 67% of patients did not demonstrate iodine uptake on any RAI scan compared to 77% in the placebo arm. Additionally, 59% of patients on the LENVIMA arm and 61% of patients on placebo arm progressed, according to RECIST 1.1, within 12 months of prior I 131 therapy; 19.2% of patients on the LENVIMA arm and 17.6% of patients on placebo arm received prior cumulative activity of >600 mCi or 22 GBq I 131, with the last dose administered at least 6 months prior to study entry. The median cumulative RAI activity administered prior to study entry was 350 mCi (12.95 GBq).

A statistically significant prolongation in PFS was demonstrated in LENVIMA-treated patients compared to those receiving placebo (Table 14 and Figure 1). Upon confirmation of progression, 83% of patients that were randomly assigned to placebo crossed over to receive open-label LENVIMA.

Table 14: Efficacy Results in Differentiated Thyroid Cancer in SELECT
 | LENVIMA N=261 | Placebo N=131
Progression-Free Survival (PFS) a
Number of events (%) | 107 (41) | 113 (86)
Progressive disease | 93 (36) | 109 (83)
Death | 14 (5) | 4 (3)
Median PFS in months (95% CI) | 18.3 (15.1, NE) | 3.6 (2.2, 3.7)
Hazard ratio (95% CI)b | 0.21 (0.16, 0.28)
p-valuec | <0.001
Objective Response Ratea
Objective response rate | 65% | 2%
(95% CI) | (59%, 71%) | (0%, 4%)
Complete response | 2% | 0%
Partial response | 63% | 2%
p-valued | <0.001
Overall Survival (OS)e
Number of deaths (%) | 71 (27) | 47 (36)
Median OS in months (95% CI) | NE (22.1, NE) | NE (20.3, NE)
Hazard ratio (95% CI)b | 0.73 (0.50, 1.07)
p-valueb | 0.10
a. Independent radiologic review
b. Estimated with Cox proportional hazard model stratified by region (Europe vs North America vs other), age group (≤65 years vs >65 years), and previous VEGF/VEGFR-targeted therapy (0 vs 1)
c. Log-rank test stratified by region (Europe vs North America vs other), age group (≤65 years vs >65 years), and previous VEGF/VEGFR-targeted therapy (0 vs 1)
d. Cochran-Mantel-Haenszel chi-square test
e. NE = Not estimable

Figure 1: Kaplan-Meier Curves for Progression-Free Survival in SELECT

14.2 Renal Cell Carcinoma

First-Line Treatment of Patients with RCC in Combination with Pembrolizumab CLEAR

The efficacy of LENVIMA in combination with pembrolizumab was investigated in CLEAR (NCT02811861), a multicenter, open-label, randomized trial that enrolled 1069 patients with advanced RCC in the first-line setting. Patients were enrolled regardless of PD-L1 tumor expression status. Patients with active autoimmune disease or a medical condition that required immunosuppression were ineligible. Randomization was stratified by geographic region (North America and Western Europe versus “Rest of the World”) and Memorial Sloan Kettering Cancer Center (MSKCC) prognostic groups (favorable, intermediate and poor risk).

Patients were randomized (1:1:1) to one of the following treatment arms:

- LENVIMA 20 mg orally once daily in combination with pembrolizumab 200 mg intravenously every 3 weeks up to 24 months.
- LENVIMA 18 mg orally once daily in combination with everolimus 5 mg orally once daily.
- Sunitinib 50 mg orally once daily for 4 weeks then off treatment for 2 weeks.

Treatment continued until unacceptable toxicity or disease progression. Administration of LENVIMA with pembrolizumab was permitted beyond RECIST-defined disease progression if the patient was clinically stable and considered by the investigator to be deriving clinical benefit. Pembrolizumab dosing was continued for a maximum of 24 months; however, treatment with LENVIMA could be continued beyond 24 months. Assessment of tumor status was performed at baseline and then every 8 weeks.

The study population characteristics were: median age of 62 years (range: 29 to 88 years); 42% age 65 or older, 75% male; 74% White, 21% Asian, 1% Black, and 2% other races; 18% and 82% of patients had a baseline KPS of 70 to 80 and 90 to 100, respectively; patient distribution by MSKCC risk categories was 27% favorable, 64% intermediate and 9% poor. Common sites of metastases in patients were lung (68%), lymph node (45%), and bone (25%).

The major efficacy outcome measures were PFS, as assessed by independent radiologic review (IRC) according to RECIST v1.1, and OS. Additional efficacy outcome measures included confirmed ORR as assessed by IRC. At the protocol-specified interim analysis, LENVIMA in combination with pembrolizumab demonstrated statistically significant improvements in PFS, OS, and ORR compared with sunitinib. An updated OS analysis was conducted when approximately 304 deaths were observed based on the planned number of deaths for the pre-specified final analysis. Table 15 and Figures 2 and 3 summarize the efficacy results for CLEAR.

Table 15: Efficacy Results in Renal Cell Carcinoma Per IRC in CLEAR
 | LENVIMA20 mg with Pembrolizumab 200mg N=355 | Sunitinib 50mg N=357
Progression-Free Survival (PFS)
Number of events, n (%) | 160 (45%) | 205 (57%)
Progressive disease | 145 (41%) | 196 (55%)
Death | 15 (4%) | 9 (3%)
Median PFS in months (95% CI) | 23.9 (20.8, 27.7) | 9.2 (6.0, 11.0)
Hazard Ratioa (95% CI) | 0.39 (0.32, 0.49)
p-valueb | <0.0001
Overall Survival (OS)
Number of deaths, n (%) | 80 (23%) | 101 (28%)
Median OS in months (95% CI) | NR (33.6, NE) | NR (NE, NE)
Hazard Ratioa (95% CI) | 0.66 (0.49, 0.88)
p-valueb | 0.0049
Updated OS
Number of deaths, n (%) | 149 (42%) | 159 (45%)
Median OS in months (95% CI) | 53.7 (48.7, NE) | 54.3 (40.9, NE)
Hazard Ratioa (95% CI) | 0.79 (0.63, 0.99)
Objective Response Rate (Confirmed)
Objective response rate, n (%) | 252 (71%) | 129 (36%)
(95% CI) | (66, 76) | (31, 41)
Complete response rate | 16% | 4%
Partial responses rate | 55% | 32%
p-valuec | <0.0001
Tumor assessments were based on RECIST 1.1; only confirmed responses are included for ORR.
Data cutoff date = 28 Aug 2020, Updated OS cutoff date = 31 July 2022
CI = confidence interval; NE= Not estimable; NR= Not reached
a. Hazard ratio is based on a Cox Proportional Hazards Model, stratified by geographic region and MSKCC prognostic groups.
b. Two-sided p-value based on stratified log-rank test.
c. Two-sided p-value based upon CMH test.

Figure 2: Kaplan-Meier Curves for Progression-Free Survival in CLEAR

L + P = LENVIMA + Pembrolizumab; S = Sunitinib.

Figure 3: Kaplan-Meier Curves for Updated Overall Survival in CLEAR

L + P = LENVIMA + Pembrolizumab; S = Sunitinib.

KEYNOTE-B61

The efficacy of LENVIMA in combination with pembrolizumab was investigated in a multicenter, single-arm study, KEYNOTE-B61 (NCT04704219), that enrolled 160 patients with advanced or metastatic non-clear cell RCC in the first-line setting. Patients with active autoimmune disease or a medical condition that required immunosuppression were ineligible.

Patients received LENVIMA 20 mg orally once daily in combination with pembrolizumab 400 mg every 6 weeks for up to 24 months or until unacceptable toxicity or disease progression. LENVIMA could be continued as a single agent beyond 24 months until unacceptable toxicity or disease progression. Administration of LENVIMA with pembrolizumab was permitted beyond RECIST-defined disease progression if the patient was considered by the investigator to be deriving clinical benefit.

Among the 158 treated patients, the baseline characteristics were: median age of 60 years (range: 24 to 87 years); 71% male; 86% White, 8% Asian, and 3% Black; <1% Hispanic or Latino; 22% and 78% of patients had a baseline KPS of 70 to 80 and 90 to 100, respectively; histologic subtypes were 59% papillary, 18% chromophobe, 4% translocation, <1% medullary, 13% unclassified, and 6% other; patient distribution by IMDC risk categories was 35% favorable, 54% intermediate, and 10% poor. Common sites of metastases in patients were lymph node (65%), lung (35%), bone (30%), and liver (21%).

The major efficacy outcome measure was ORR as assessed by BICR using RECIST 1.1. Additional efficacy outcome measures included DOR as assessed by BICR using RECIST 1.1. Efficacy results are summarized in Table 16.

Table 16: Efficacy Results in Study (NCT04704219)

Endpoint | LENVIMA 20 mg and pembrolizumab 400 mg every 6 weeks n=158
Objective Response Rate (Confirmed)
ORR, (95% CI) | 51% (43, 59)
Complete response | 8%
Partial response | 42%
Duration of Response*
Median in months (range) | 19.5 (1.5+, 23.5+)
CI = confidence interval
* Based on Kaplan-Meier estimates
+ Denotes ongoing response

Previously Treated RCC in Combination with Everolimus (Study 205)

The efficacy was evaluated in a multicenter, randomized (1:1:1) study (Study 205: NCT01136733), in which 153 patients with advanced or metastatic renal cell carcinoma who have previously received anti-angiogenic therapy received LENVIMA 18 mg orally once daily with everolimus 5 mg orally once daily, LENVIMA 24 mg orally once daily, or everolimus 10 mg orally once daily. Patients were required to have histological confirmation of clear cell RCC and ECOG PS of 0 or 1. Patients were stratified by hemoglobin level (≤ or >13 g/dL for males and ≤ or >11.5 g/dL for females) and corrected serum calcium (≥10 mg/dL vs. <10 mg/dL). The major efficacy outcome measure was investigator-assessed PFS evaluated according to RECIST 1.1.

Of the 101 patients randomized to the LENVIMA with everolimus arm or everolimus arm, 72% were male, the median age was 60 years, 31% were older than 65 years, and 96% were White. Metastases were present in 95% of the patients and unresectable advanced disease was present in 5%. All patients had a baseline ECOG PS of either 0 (54%) or 1 (46%) with similar distribution across these two treatment arms. MSKCC favorable, intermediate, and poor risk categories were observed, respectively, in 24%, 37%, and 39% of patients in the LENVIMA with everolimus arm and 24%, 38%, and 38% of patients in the everolimus arm.

Efficacy results from Study 205 are summarized in Table 17 and Figures 4 and 5. The treatment effect of the combination on PFS was supported by a retrospective independent review of radiographs with an observed hazard ratio (HR) of 0.43 (95% CI: 0.24, 0.75) compared with the everolimus arm.

Table 17: Efficacy Results in Renal Cell Carcinoma Per Investigator Assessment in Study 205
 | LENVIMA 18 mg with Everolimus 5 mg N=51 | Everolimus 10 mg N=50
Progression-Free Survival (PFS) a
Number of events, n (%) | 26 (51) | 37 (74)
Progressive disease | 21 (41) | 35 (70)
Death | 5 (10) | 2 (4)
Median PFS in months (95% CI) | 14.6 (5.9, 20.1) | 5.5 (3.5, 7.1)
Hazard Ratio (95% CI)b LENVIMA with Everolimus vs Everolimus | 0.37 (0.22, 0.62) | -
Overall Survival (OS) c
Number of deaths, n (%) | 32 (63) | 37 (74)
Median OS in months (95% CI) | 25.5 (16.4, 32.1) | 15.4 (11.8, 20.6)
Hazard Ratio (95% CI)b LENVIMA with Everolimus vs Everolimus | 0.67 (0.42, 1.08) | -
Objective Response Rate (Confirmed)
Objective response rate, n (%) | 19 (37) | 3 (6)
(95% CI) | (24, 52) | (1, 17)
Number of complete responses, n (%) | 1 (2) | 0
Number of partial responses (%) | 18 (35) | 3 (6)
Tumor assessments were based on RECIST v1.1 criteria for progression but only confirmed responses are included for ORR. Data cutoff date = 13 Jun 2014
CI = confidence interval
a. Point estimates are based on Kaplan-Meier method and 95% CIs are based on the Greenwood formula using log-log transformation.
b. Hazard ratio is based on a stratified Cox regression model including treatment as a covariate factor and hemoglobin and corrected serum calcium as strata.
c. Data cutoff date = 31 Jul 2015

Figure 4: Kaplan-Meier Curves for Progression-Free Survival

in Study 205

Figure 5: Kaplan-Meier Curves for Overall Survival in Study 205

14.3 Hepatocellular Carcinoma

The efficacy of LENVIMA was evaluated in a randomized, open-label, multicenter, international study (REFLECT; NCT01761266) conducted in patients with previously untreated unresectable hepatocellular carcinoma (HCC). The study enrolled adults with Child-Pugh A and Barcelona Clinic Liver Cancer (BCLC) Stage C or B HCC who were ineligible for local liver-directed therapy; had an ECOG PS of 0 or 1; had received no prior systemic therapy for HCC; and had at least one measurable target lesion according to modified RECIST for HCC.

Patients were randomized (1:1) to receive LENVIMA (12 mg for baseline body weight ≥60 kg or 8 mg for baseline body weight <60 kg) orally once daily or sorafenib 400 mg orally twice daily until radiological disease progression or unacceptable toxicity. Randomization was stratified by region (Western vs Asia Pacific), presence of macroscopic portal vein invasion or extrahepatic spread (yes vs no), ECOG PS (0 vs 1), and body weight (<60 kg vs ≥60 kg). The major efficacy outcome measure was overall survival (OS). REFLECT was designed to show the non-inferiority of LENVIMA to sorafenib for OS. Additional efficacy outcome measures were progression-free survival (PFS) and objective response rate (ORR) according to modified RECIST for HCC.

A total of 954 patients were randomized, 478 to the LENVIMA arm and 476 to the sorafenib arm. The demographics of the study population were: median age of 62 years (range: 20 to 88 years); 84% male; 69% Asian and 29% White; 63% ECOG PS of 0; and 69% weighed ≥60 kg. Of the 590 (62%) patients with at least one site of documented distant metastatic disease, 52% had lung metastasis, 45% had lymph node metastasis, and 16% had bone metastasis.

Macroscopic portal vein invasion, extra-hepatic spread, or both were present in 70% of patients. HCC was categorized as Child-Pugh A and BCLC Stage C in 79% and Child-Pugh A and BCLC Stage B in 21% of patients. Seventy-five percent (75%) of patients had radiographic evidence of cirrhosis at baseline. Investigator-documented primary risk factors for the development of HCC were hepatitis B (50%), hepatitis C (23%), alcohol use (6%), other (7%), and unknown (14%).

REFLECT demonstrated that LENVIMA was non-inferior to sorafenib for OS. REFLECT did not demonstrate a statistically significant improvement in OS for patients randomized to LENVIMA as compared to those in the sorafenib arm. LENVIMA was statistically significantly superior to sorafenib for PFS and ORR. Efficacy results are summarized in Table 18 and Figure 6.

Table 18: Efficacy Results in Hepatocellular Carcinoma in REFLECT
 | LENVIMA N= 478 | Sorafenib N=476
Overall Survival
Number of deaths (%) | 351 (73) | 350 (74)
Median OS in months (95% CI) | 13.6 (12.1, 14.9) | 12.3 (10.4, 13.9)
Hazard Ratio (95% CI)a | 0.92 (0.79, 1.06)
Progression-Free Survivalb (mRECIST)
Number of Events (%) | 311 (65) | 323 (68)
Median PFS in months (95% CI) | 7.3 (5.6, 7.5) | 3.6 (3.6, 3.7)
Hazard Ratio (95% CI) | 0.64 (0.55, 0.75)
p-value | <0.001
Objective Response Rateb (mRECIST)
Objective response rate | 41% | 12%
Complete responses, n (%) | 10 (2.1) | 4 (0.8)
Partial responses, n (%) | 184 (38.5) | 55 (11.6)
95% CI | (36%, 45%) | (10%, 16%)
p-value | <0.001
Progression-Free Survivalb (RECIST 1.1)
Number of Events (%) | 307 (64) | 320 (67)
Median PFS in months (95% CI) | 7.3 (5.6, 7.5) | 3.6 (3.6, 3.9)
Hazard Ratio (95% CI) | 0.65 (0.56, 0.77)
Objective Response Rateb (RECIST 1.1)
Objective response rate | 19% | 7%
Complete responses, n (%) | 2 (0.4) | 1 (0.2)
Partial responses, n (%) | 88 (18.4) | 30 (6.3)
95% CI | (15%, 22%) | (4%, 9%)
CI = confidence interval; ECOG PS = Eastern Cooperative Oncology Group Performance Status; HR = hazard ratio; OS = overall survival.
a. Based on stratified Cox-model. Non-inferiority margin for HR (LENVIMA vs sorafenib) is 1.08.
b. Per independent radiology review.

Figure 6: Kaplan-Meier Curves for Overall Survival in REFLECT

14.4 Endometrial Carcinoma (EC)

The efficacy of LENVIMA in combination with pembrolizumab was investigated in Study 309 (NCT03517449), a multicenter, open-label, randomized, active-controlled trial that enrolled 827 patients with advanced endometrial carcinoma who had been previously treated with at least one prior platinum-based chemotherapy regimen in any setting, including in the neoadjuvant and adjuvant settings. Patients with endometrial sarcoma, including carcinosarcoma, or patients who had active autoimmune disease or a medical condition that required immunosuppression were ineligible. Patients with endometrial carcinoma that were pMMR (using the VENTANA MMR RxDx Panel test) or not MSI-H were stratified by ECOG performance status, geographic region, and history of pelvic radiation. Patients were randomized (1:1) to one of the following treatment arms:

- LENVIMA 20 mg orally once daily in combination with pembrolizumab 200 mg intravenously every 3 weeks.
- Investigator’s choice consisting of either doxorubicin 60 mg/m^2 every 3 weeks, or paclitaxel 80 mg/m^2 given weekly, 3 weeks on/1 week off.

Treatment with LENVIMA and pembrolizumab continued until RECIST v1.1-defined progression of disease as verified by BICR, unacceptable toxicity, or for pembrolizumab, a maximum of 24 months. Treatment was permitted beyond RECIST v1.1-defined disease progression if the treating investigator considered the patient to be deriving clinical benefit and the treatment was tolerated. Assessment of tumor status was performed every 8 weeks. The major efficacy outcome measures were OS and PFS as assessed by BICR according to RECIST v1.1, modified to follow a maximum of 10 target lesions and a maximum of 5 target lesions per organ. Additional efficacy outcome measures included ORR and DOR, as assessed by BICR.

Among the 697 pMMR or not MSI-H patients, 346 patients were randomized to LENVIMA in combination with pembrolizumab, and 351 patients were randomized to investigator’s choice of doxorubicin (n=254) or paclitaxel (n=97). The population characteristics of these patients were: median age of 65 years (range: 30 to 86), 52% age 65 or older; 62% White, 22% Asian, and 3% Black; 60% ECOG PS of 0 and 40% ECOG PS of 1. The histologic subtypes were endometrioid carcinoma (55%), serous (30%), clear cell carcinoma (7%), mixed (4%), and other (3%). All 697 of these patients received prior systemic therapy for endometrial carcinoma: 67% had one, 30% had two, and 3% had three or more prior systemic therapies. Thirty-seven percent of patients received only prior neoadjuvant or adjuvant therapy.

Efficacy results for these patients are summarized in Table 19 and Figures 7 and 8.

Table 19: Efficacy Results in Endometrial Carcinoma in Study 309
 | Endometrial Carcinoma (pMMR or not MSI-H)
Endpoint | LENVIMA with pembrolizumab N=346 | Doxorubicin or Paclitaxel N=351
OS
Number (%) of patients with event | 165 (48%) | 203 (58%)
Median in months (95% CI) | 17.4 (14.2, 19.9) | 12.0 (10.8, 13.3)
Hazard ratioa (95% CI) | 0.68 (0.56, 0.84)
p-valueb | 0.0001
PFSc
Number (%) of patients with event | 247 (71%) | 238 (68%)
Median in months (95% CI) | 6.6 (5.6, 7.4) | 3.8 (3.6, 5.0)
Hazard ratioa (95% CI) | 0.60 (0.50, 0.72)
p-valueb | <0.0001
Objective Response Rate
ORRc (95% CI) | 30% (26, 36) | 15% (12,19)
Complete response | 5% | 3%
Partial response | 25% | 13%
p-valued | <0.0001
Duration of Response | N=105 | N=53
Median in months (range) | 9.2 (1.6+, 23.7+) | 5.7 (0.0+, 24.2+)
a Based on the stratified Cox regression model
b Based on stratified log-rank test
c Per independent radiology review
d Based on Miettinen and Nurminen method stratified by ECOG performance status, geographic region, and history of pelvic radiation

Figure 7: Kaplan-Meier Curves for Overall Survival in Study 309

(pMMR or not MSI-H)

Figure 8: Kaplan-Meier Curves for Progression-Free Survival in Study 309

(pMMR or not MSI-H)

16 HOW SUPPLIED/STORAGE AND HANDLING

LENVIMA 4 mg capsules are supplied as hard hypromellose capsules with yellowish-red body and yellowish-red cap, marked in black ink with “Є” on the cap and “LENV 4 mg” on the body.

LENVIMA 10 mg capsules are supplied as hard hypromellose capsules with yellow body and yellowish-red cap, marked in black ink with “Є” on the cap and “LENV 10 mg” on the body.

LENVIMA capsules are supplied in cartons of 6 cards. Each card is a 5-day blister card as follows:

- NDC 62856-724-30: 24 mg, carton with 6 cards NDC 62856-724-05 (ten 10 mg capsules and five 4 mg capsules per card).
- NDC 62856-720-30: 20 mg, carton with 6 cards NDC 62856-720-05 (ten 10 mg capsules per card).
- NDC 62856-718-30: 18 mg, carton with 6 cards NDC 62856-718-05 (five 10 mg capsules and ten 4 mg capsules per card).
- NDC 62856-714-30: 14 mg, carton with 6 cards NDC 62856-714-05 (five 10 mg capsules and five 4 mg capsules per card).
- NDC 62856-712-30: 12 mg, carton with 6 cards NDC 62856-712-05 (fifteen 4 mg capsules per card).
- NDC 62856-710-30: 10 mg, carton with 6 cards NDC 62856-710-05 (five 10 mg capsules per card).
- NDC 62856-708-30: 8 mg, carton with 6 cards NDC 62856-708-05 (ten 4 mg capsules per card).
- NDC 62856-704-30: 4 mg, carton with 6 cards NDC 62856-704-05 (five 4 mg capsules per card).

Store at 20°C to 25°C (68°F to 77°F); excursions permitted to 15°C to 30°C (59°F to 86°F) [see USP Controlled Room Temperature].

17 PATIENT COUNSELING INFORMATION

Advise the patient to read the FDA-approved patient labeling (Patient Information).

Hypertension

Advise patients to undergo regular blood pressure monitoring and to contact their health care provider if blood pressure is elevated [see Warnings and Precautions (5.1)].

Cardiac Dysfunction

Advise patients that LENVIMA can cause cardiac dysfunction and to immediately contact their healthcare provider if they experience any clinical symptoms of cardiac dysfunction [see Warnings and Precautions (5.2)].

Arterial Thrombotic Events

Advise patients to seek immediate medical attention for new onset chest pain or acute neurologic symptoms consistent with myocardial infarction or stroke [see Warnings and Precautions (5.3)].

Hepatotoxicity

Advise patients that they will need to undergo laboratory tests to monitor liver function and to report any new symptoms indicating hepatic toxicity or failure [see Warnings and Precautions (5.4)].

Proteinuria and Renal Failure/Impairment

Advise patients that they will need to undergo regular laboratory tests to monitor kidney function and protein in the urine [see Warnings and Precautions (5.5, 5.6)].

Diarrhea

Advise patients when to start standard anti-diarrheal therapy and to maintain adequate hydration. Advise patients to contact their healthcare provider if they are unable to maintain adequate hydration [see Warnings and Precautions (5.7)].

Fistula Formation and Gastrointestinal Perforation

Advise patients that LENVIMA can increase the risk of fistula formation or gastrointestinal perforation and to seek immediate medical attention for severe abdominal pain [see Warnings and Precautions (5.8)].

QTc Interval Prolongation

Advise patients who are at risk for QTc prolongation that they will need to undergo regular ECGs. Advise all patients that they will need to undergo laboratory tests to monitor electrolytes [see Warnings and Precautions (5.9)].

Hypocalcemia

Advise patients of the risks of hypocalcemia, that they will need to undergo laboratory tests to monitor calcium levels, and the potential requirement for calcium supplementation [see Warnings and Precautions (5.10)].

Reversible Posterior Leukoencephalopathy Syndrome (RPLS)

Advise patients of the signs and symptoms of RPLS and to contact their healthcare provider for new onset or worsening neurological function [see Warnings and Precautions (5.11)].

Hemorrhagic Events

Advise patients that LENVIMA can increase the risk for bleeding and to contact their healthcare provider for bleeding or symptoms of severe bleeding [see Warnings and Precautions (5.12)].

Impairment of Thyroid Stimulating Hormone Suppression/Thyroid Dysfunction

Advise patients that LENVIMA can cause hypothyroidism and that their thyroid function should be monitored regularly during treatment [see Warnings and Precautions (5.13)].

Impaired Wound Healing

Advise patients that LENVIMA may impair wound healing. Advise patients to inform their healthcare provider of any planned surgical procedure [see Warnings and Precautions (5.14)].

Osteonecrosis of the Jaw (ONJ)

Advise patients regarding good oral hygiene practices and to have preventive dentistry performed prior to treatment with LENVIMA and throughout treatment with LENVIMA. Inform patients being treated with LENVIMA, particularly those who are at high risk for ONJ, to avoid invasive dental procedures, if possible, and to inform their healthcare provider of any planned dental procedures [see Warnings and Precautions (5.15)]. Advise patients to immediately contact their healthcare provider for signs or symptoms associated with ONJ.

Embryo-Fetal Toxicity

Advise females of reproductive potential of the potential risk to a fetus and to inform their healthcare provider of a known or suspected pregnancy [see Warnings and Precautions (5.16), Use in Specific Populations (8.1)].

Advise females of reproductive potential to use effective contraception during treatment with LENVIMA and for 30 days after the last dose [see Use in Specific Populations (8.3)].

Lactation

Advise women to discontinue breastfeeding during treatment with LENVIMA and for 1 week after the last dose [see Use in Specific Populations (8.2)].

Distributed by:
Eisai Inc.
Nutley, NJ 07110

LENVIMA® is a registered trademark of Eisai R&D Management Co., Ltd. and is licensed to Eisai Inc.

© 2015-2025 Eisai Inc.

PATIENT INFORMATION
LENVIMA® (lehn-veema)
(lenvatinib)
capsules

What is LENVIMA?
LENVIMA is a prescription medicine that is used to treat people with certain kinds of cancer.

- LENVIMA is used by itself to treat differentiated thyroid cancer (DTC), a type of thyroid cancer that can no longer be treated with radioactive iodine and is progressing.
- LENVIMA is used to treat adults with a type of kidney cancer called advanced renal cell carcinoma (RCC):
  ○ along with the medicine pembrolizumab as your first treatment when your kidney cancer has spread or cannot be removed by surgery.
  ○ along with the medicine everolimus after one course of treatment with another anti-cancer medicine (anti-angiogenic therapy).
- LENVIMA is used by itself as the first treatment for a type of liver cancer called hepatocellular carcinoma (HCC) when it cannot be removed by surgery.
- LENVIMA is used along with another medicine called pembrolizumab to treat advanced endometrial carcinoma (EC), a type of uterine cancer:
  ○ when a laboratory test shows that your tumor is mismatch repair proficient (pMMR) or not microsatellite instability-high (MSI-H), and
  ○ you have received anti-cancer treatment, and it is no longer working, and
  ○ your cancer cannot be cured by surgery or radiation.

The safety and efficacy of LENVIMA have not been established in children.

Before you take LENVIMA, tell your healthcare provider about all of your medical conditions, including if you:

- have high blood pressure
- have heart problems
- have a history of blood clots in your arteries (type of blood vessel), including stroke, heart attack, or change in vision
- have or have had liver or kidney problems
- have a history of a tear (perforation) in your stomach or intestine, or an abnormal connection between two or more body parts (fistula)
- have headaches, seizures, or vision problems
- have any bleeding problems
- plan to have surgery, a dental procedure, or have had a recent surgery. You should stop taking LENVIMA at least 1 week before planned surgery. See “What are the possible side effects of LENVIMA?”
- are pregnant or plan to become pregnant. LENVIMA can harm your unborn baby.
  Females who are able to become pregnant:
  ○ Your healthcare provider should do a pregnancy test before you start treatment with LENVIMA.
  ○ You should use an effective method of birth control (contraception) during treatment with LENVIMA and for 30 days after the last dose of LENVIMA. Talk with your healthcare provider about birth control methods you can use during this time. Tell your healthcare provider right away if you become pregnant or think you are pregnant during treatment with LENVIMA.
- are breastfeeding or plan to breastfeed. It is not known if LENVIMA passes into your breast milk. Do not breastfeed during treatment with LENVIMA and for 1 week after the last dose.

Tell your healthcare provider about all the medicines you take, including prescription and over-the-counter medicines, vitamins, and herbal supplements.
Especially tell your healthcare provider if you are taking, or have taken, an osteoporosis medicine.
Know the medicines you take. Keep a list of your medicines to show to your healthcare provider and pharmacist when you get a new medicine.

How should I take LENVIMA?

- Take LENVIMA exactly as your healthcare provider tells you to take it.
- Your healthcare provider will tell you how much LENVIMA to take and when to take it. Your healthcare provider may change your dose during treatment, stop treatment for some time, or completely stop treatment with LENVIMA if you have side effects.
- Take LENVIMA 1 time each day at the same time, with or without food.
- If you miss a dose of LENVIMA, take it as soon as you remember. If your next dose is due within 12 hours, skip the missed dose and take the next dose at your regular time.
- Swallow LENVIMA capsules whole. Do not crush or chew the LENVIMA capsules.
- If you cannot swallow LENVIMA capsules whole, LENVIMA capsules can be mixed with water or apple juice,then taken by mouth, or mixed with water and given through a feeding tube.
- If you take too much LENVIMA, call your healthcare provider or go to the nearest hospital emergency room right away.

How to take LENVIMA by mouth if you cannot swallow whole capsules:

- Place your daily dose, up to 5 capsules, in a small container or oral syringe (approximately 20 mL capacity).
- Add 3 mL of water or apple juice to the container or oral syringe. Wait 10 minutes for the capsule shell (outer surface) to dissolve completely, then stir or shake the mixture for 3 minutes until capsules are fully dissolved. Do not break or crush the capsules.
- Drink the liquid mixture or use an oral syringe to take directly into the mouth.
- Next, using a second syringe, add an additional 2 mL of liquid to the container or oral syringe (cap the first oral syringe before adding the additional water) then swirl or shake and take the liquid mixture. Repeat this step at least one time and until you cannot see any of the LENVIMA mixture left in the container or oral syringe to make sure all of the medicine is taken.
- If 6 capsules are required for your daily dose, follow the above instructions using 3 capsules at a time.

How to give LENVIMA through a feeding tube:

- LENVIMA should be given in feeding tubes of at least 5 French diameter (polyvinyl chloride or polyurethane tube) and at least 6 French diameter (silicone tube).
  ○ Place your daily dose, up to 5 capsules, in a syringe (20 mL capacity).
  ○ Add 3 mL of water to the syringe. Wait 10 minutes for the capsule shell (outer surface) to dissolve completely, then stir or shake the mixture for 3 minutes until capsules are fully dissolved. Do not break or crush the capsules.
  ○ Give the mixture through a feeding tube.
  ○ Next, cap the syringe and remove the plunger. Use a second syringe and add an additional 2 mL of liquid to the syringe. Swirl or shake and give the mixture in the feeding tube. Repeat this step at least one time and until you cannot see any of the LENVIMA mixture left in the syringe to make sure all of the medicine is taken.
  ○ If 6 capsules are required for your daily dose, follow the above instructions using 3 capsules at a time.
- LENVIMA mixture may be stored in a covered container in the refrigerator at 36ºF to 46ºF (2ºC to 8ºC) for a maximum of 24 hours. Throw away the LENVIMA mixture if not used within 24 hours of mixing.

What are the possible side effects of LENVIMA?
LENVIMA may cause serious side effects, including:

- High blood pressure (hypertension). High blood pressure is a common side effect of LENVIMA and can be serious. Your blood pressure should be well controlled before you start taking LENVIMA. Your healthcare provider should check your blood pressure regularly during treatment with LENVIMA. If you develop blood pressure problems, your healthcare provider may prescribe medicine to treat your high blood pressure.
- Heart problems. LENVIMA can cause serious heart problems that may lead to death. Call your healthcare provider right away if you get symptoms of heart problems, such as shortness of breath or swelling of your ankles.
- Problem with blood clots in your blood vessels (arteries). Get emergency medical help right away if you get any of the following symptoms:

- severe chest pain or pressure
- pain in your arms, back, neck or jaw
- shortness of breath
- numbness or weakness on one side of your body

- trouble talking
- sudden severe headache
- sudden vision changes

- Liver problems. LENVIMA may cause liver problems that may lead to liver failure and death. Your healthcare provider will check your liver function before and during treatment with LENVIMA. Tell your healthcare provider right away if you develop any of the following symptoms:
  ○ your skin or the white part of your eyes turns yellow (jaundice)
  ○ dark “tea colored” urine
  ○ light-colored bowel movements (stools)
  ○ feeling drowsy, confused or loss of consciousness
- Kidney problems. Kidney failure, which can lead to death, has happened with LENVIMA treatment. Your healthcare provider should do regular blood tests to check your kidneys.
- Increased protein in your urine (proteinuria). Proteinuria is a common side effect of LENVIMA and can be serious. Your healthcare provider should check your urine for protein before and during your treatment with LENVIMA.
- Diarrhea. Diarrhea is a common side effect of LENVIMA and can be serious. If you get diarrhea, ask your healthcare provider about what medicines you can take to treat your diarrhea. It is important to drink more water when you get diarrhea. Tell your healthcare provider or go to the emergency room if you are unable to drink enough liquids and your diarrhea is not able to be controlled.
- An opening in the wall of your stomach or intestines (perforation) or an abnormal connection between two or more body parts (fistula). Get emergency medical help right away if you develop severe stomach (abdomen) pain.
- Changes in the electrical activity of your heart called QT prolongation. QT prolongation can cause irregular heartbeats that can be life threatening. Your healthcare provider will do blood tests before and during your treatment with LENVIMA to check the levels of potassium, magnesium, and calcium in your blood, and may check the electrical activity of your heart with an electrocardiogram (ECG).
- Low levels of blood calcium (hypocalcemia). Your healthcare provider will check your blood calcium levels during treatment with LENVIMA and may tell you to take a calcium supplement if your calcium levels are low.
- A condition called Reversible Posterior Leukoencephalopathy Syndrome (RPLS). Call your healthcare provider right away if you get severe headache, seizures, weakness, confusion, or blindness or change in vision.
- Bleeding. LENVIMA may cause serious bleeding problems that may lead to death. Tell your healthcare provider if you develop any signs or symptoms of bleeding during treatment with LENVIMA, including:

- severe and persistent nose bleeds
- vomiting blood
- red or black (looks like tar) stools

- blood in your urine
- coughing up blood or blood clots
- heavy or new onset vaginal bleeding

- Change in thyroid hormone levels. Your healthcare provider should check your thyroid hormone levels before starting and every month during treatment with LENVIMA.
- Wound healing problems. Wound healing problems have happened in some people who take LENVIMA. Tell your healthcare provider if you plan to have any surgery before or during treatment with LENVIMA.
  ○ You should stop taking LENVIMA at least 1 week before planned surgery.
  ○ Your healthcare provider should tell you when you may start taking LENVIMA again after surgery.
- Severe jawbone problems (osteonecrosis). Severe jawbone problems have happened in some people who take LENVIMA. Certain risk factors such as taking a bisphosphonate medicine or the medicine denosumab, having dental disease, or an invasive dental procedure may increase your risk of getting jawbone problems. Your healthcare provider should examine your mouth before you start and during treatment with LENVIMA. Tell your dentist that you are taking LENVIMA. It is important for you to practice good mouth care during treatment with LENVIMA. Tell your healthcare provider right away if you get signs or symptoms of jawbone problems during treatment with LENVIMA, including jaw pain, toothache, or sores on your gums. Tell your healthcare provider if you plan to have any dental procedures before or during treatment with LENVIMA. You should avoid having invasive dental procedures if possible, during treatment with LENVIMA. Stopping your bisphosphonate medicine before an invasive dental procedure may help decrease your risk of getting these jaw problems.
  ○ You should stop taking LENVIMA at least 1 week before planned dental surgery or invasive dental procedures.
  ○ Your healthcare provider should tell you when you may start taking LENVIMA again after dental procedures.

The most common side effects of LENVIMA in people treated for thyroid cancer include:

- tiredness
- joint and muscle pain
- decreased appetite
- weight loss
- nausea
- mouth sores

- headache
- vomiting
- rash, redness, itching, or peeling of your skin on your hands and feet
- stomach (abdomen) pain
- hoarseness

The most common side effects of LENVIMA in people treated for kidney cancer in combination with everolimus include:

- tiredness
- joint and muscle pain
- decreased appetite
- vomiting
- nausea
- mouth sores
- swelling in your arms and legs

- cough
- stomach (abdomen) pain
- trouble breathing
- rash
- weight loss
- bleeding

The most common side effects of LENVIMA in people treated for liver cancer include:

- tiredness
- decreased appetite
- joint and muscle pain
- weight loss
- stomach (abdomen) pain

- rash, redness, itching, or peeling of your skin on your hands and feet
- hoarseness
- bleeding
- decrease in thyroid hormone levels
- nausea

The most common side effects of LENVIMA when given in combination with pembrolizumab include:

- decrease in thyroid hormone levels
- tiredness
- joint and muscle pain
- nausea
- decreased appetite
- vomiting
- mouth sores

- weight loss
- stomach-area (abdomen) pain
- urinary tract infection
- constipation
- headache
- bleeding
- rash, redness, itching, or peeling of your skin on your hands and feet
- hoarseness
- rash

LENVIMA may cause fertility problems in males and females. Talk to your healthcare provider if this is a concern for you.
Your healthcare provider may need to reduce your dose of LENVIMA, or delay or completely stop treatment, if you have certain side effects.
These are not all the possible side effects of LENVIMA.
Call your doctor for medical advice about side effects. You may report side effects to FDA at 1-800-FDA-1088.

How should I store LENVIMA?

- Store LENVIMA at room temperature, between 68°F to 77°F (20°C to 25°C).
- Keep LENVIMA and all medicines out of the reach of children.

General information about the safe and effective use of LENVIMA.
Medicines are sometimes prescribed for purposes other than those listed in a Patient Information leaflet. Do not use LENVIMA for a condition for which it was not prescribed. Do not give LENVIMA to other people, even if they have the same symptoms you have. It may harm them. You can ask your healthcare provider or pharmacist for information about LENVIMA that is written for health professionals.

What are the ingredients in LENVIMA?
Active ingredient: lenvatinib
Inactive ingredients: calcium carbonate, hydroxypropyl cellulose, low-substituted hydroxypropylcellulose, mannitol, microcrystalline cellulose, and talc.
The capsule shell contains: ferric oxide red, ferric oxide yellow, hypromellose, and titanium dioxide. The printing ink contains black iron oxide, potassium hydroxide, propylene glycol and shellac.
Distributed by: Eisai Inc., Nutley, NJ 07110
LENVIMA® is a registered trademark of Eisai R&D Management Co., Ltd. and is licensed to Eisai Inc.
For more information, call 1-877-873-4724 or go to www.LENVIMA.com.
© 2015-2024 Eisai Inc.

This Patient Information has been approved by the U.S. Food and Drug Administration. Revised: 04/2024

PACKAGE LABEL

PRINCIPAL DISPLAY PANEL

NDC 62856-704-30
Lenvima
(lenvatinib) capsules
4 mg daily dose

PACKAGE LABEL

PRINCIPAL DISPLAY PANEL

NDC 62856-708-30
Lenvima
(lenvatinib) capsules
8 mg daily dose

PACKAGE LABEL

PRINCIPAL DISPLAY PANEL

NDC 62856-710-30
Lenvima
(lenvatinib) capsules
10 mg daily dose
30 day supply
10 mg daily-dose carton containing 6 cards

PACKAGE LABEL

PRINCIPAL DISPLAY PANEL

NDC 62856-712-30
Lenvima
(lenvatinib) capsules
12 mg daily dose

PACKAGE LABEL

PRINCIPAL DISPLAY PANEL

NDC 62856-714-30
Lenvima
(lenvatinib) capsules
14 mg daily dose
30 day supply
14 mg daily-dose carton containing 6 cards

PACKAGE LABEL

PRINCIPAL DISPLAY PANEL

NDC 62856-718-30
Lenvima
(lenvatinib) capsules
18 mg daily dose

30 day supply
18 mg daily-dose carton containing 6 cards

PACKAGE LABEL

PRINCIPAL DISPLAY PANEL

NDC 62856-720-30
Lenvima
(lenvatinib) capsules
20 mg daily dose
30 day supply
20 mg daily-dose carton containing 6 cards

PACKAGE LABEL

PRINCIPAL DISPLAY PANEL

NDC 62856-724-30
Lenvima
(lenvatinib) capsules
24 mg daily dose
30 day supply
24 mg daily- dose carton containing 6 cards

PACKAGE LABEL

PRINCIPAL DISPLAY PANEL

NDC 62856-704-05
Lenvima
(lenvatinib) capsules
4 mg daily dose

PACKAGE LABEL

PRINCIPAL DISPLAY PANEL

NDC 62856-708-05
Lenvima
(lenvatinib) capsules
8 mg daily dose

PACKAGE LABEL

PRINCIPAL DISPLAY PANEL

NDC 62856-710-05
Lenvima
(lenvatinib) capsules
10 mg daily dose

PACKAGE LABEL

PRINCIPAL DISPLAY PANEL

NDC 62856-712-05
Lenvima
(lenvatinib) capsules
12 mg daily dose

PACKAGE LABEL

PRINCIPAL DISPLAY PANEL

NDC 62856-714-05
Lenvima
(lenvatinib) capsules
14 mg daily dose

PACKAGE LABEL

PRINCIPAL DISPLAY PANEL

NDC 62856-718-05
Lenvima
(lenvatinib) capsules
18 mg daily dose

PACKAGE LABEL

PRINCIPAL DISPLAY PANEL

NDC 62856-720-05
Lenvima
(lenvatinib) capsules
20 mg daily dose

PACKAGE LABEL

PRINCIPAL DISPLAY PANEL

NDC 62856-724-05
Lenvima
(lenvatinib) capsules
24 mg daily dose